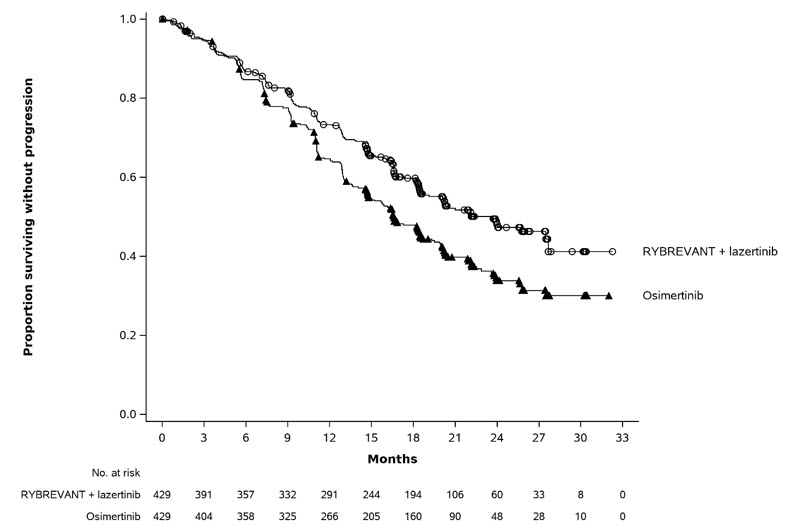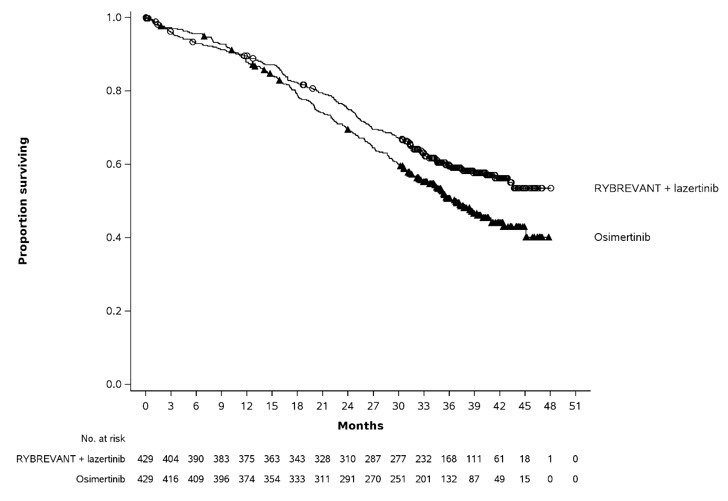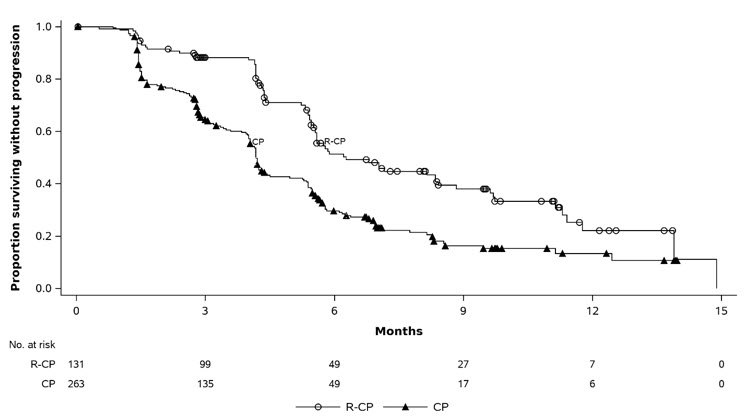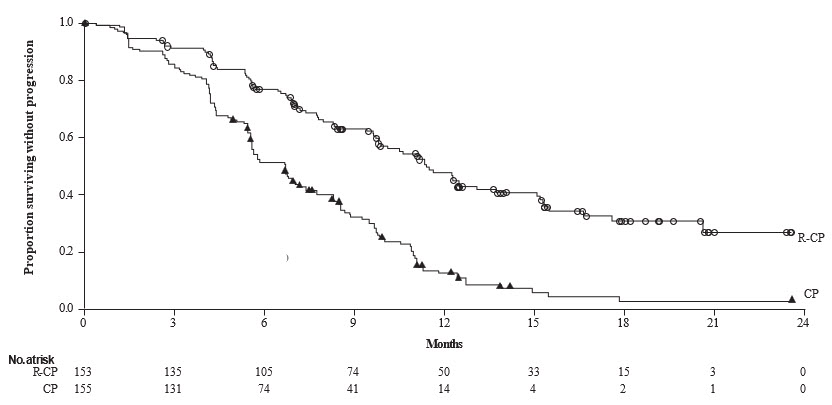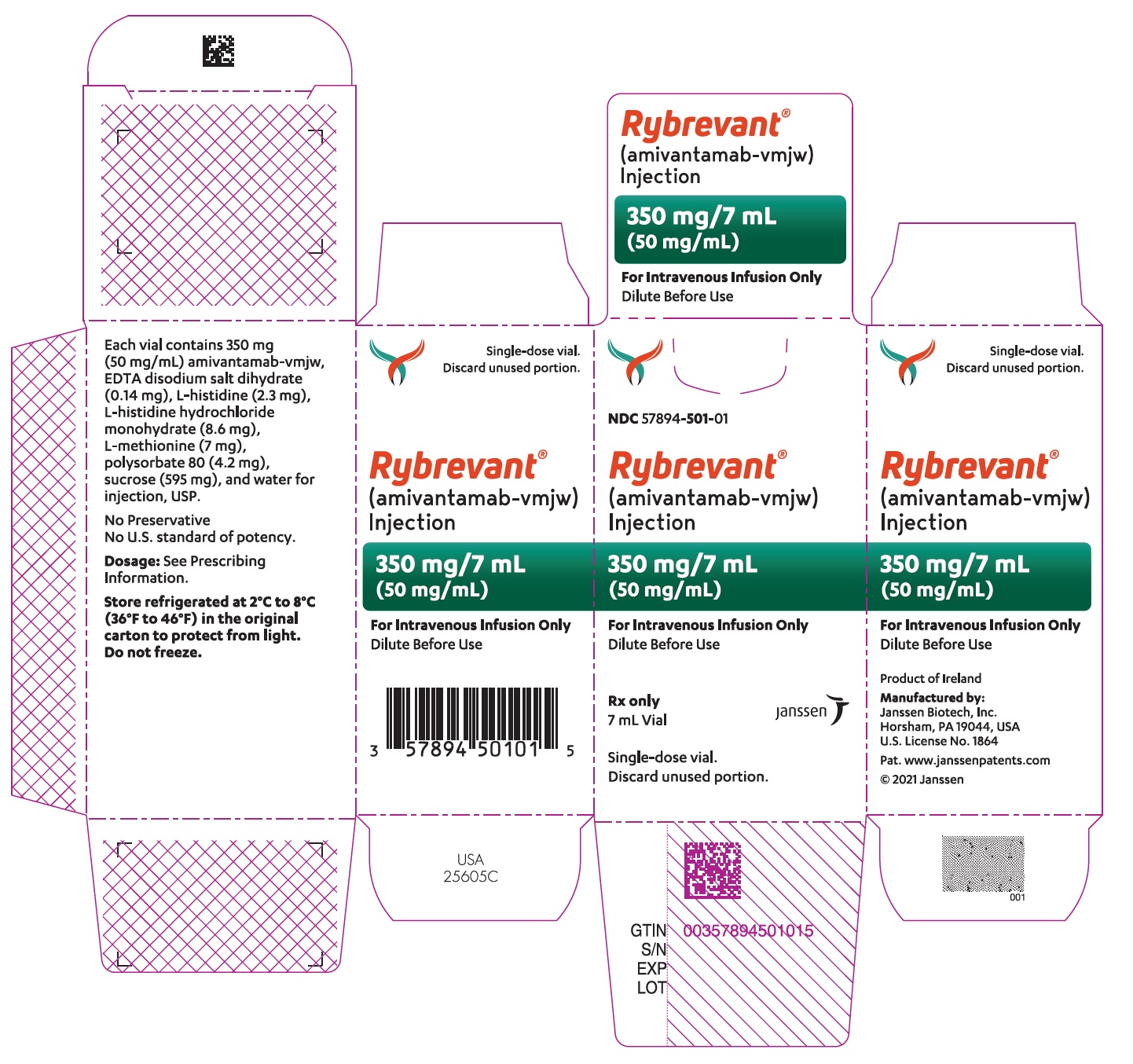 DRUG LABEL: Rybrevant
NDC: 57894-501 | Form: INJECTION
Manufacturer: Janssen Biotech, Inc.
Category: prescription | Type: HUMAN PRESCRIPTION DRUG LABEL
Date: 20251111

ACTIVE INGREDIENTS: AMIVANTAMAB 350 mg/1 1
INACTIVE INGREDIENTS: EDETATE DISODIUM; HISTIDINE; HISTIDINE HYDROCHLORIDE MONOHYDRATE; METHIONINE; POLYSORBATE 20; SUCROSE; WATER

HIGHLIGHTS OF PRESCRIBING INFORMATION

These highlights do not include all the information needed to use RYBREVANT safely and effectively. See full prescribing information for RYBREVANT.
RYBREVANT® (amivantamab-vmjw) injection, for intravenous use
Initial U.S. Approval: 2021

RECENT MAJOR CHANGES

Dosage and Administration (2.5) | 09/2025
Dosage and Administration (2.6) | 11/2025
Dosage and Administration (2.8) | 02/2025
Warnings and Precautions (5.1) | 02/2025
Warnings and Precautions (5.4) | 11/2025

1 INDICATIONS AND USAGE

RYBREVANT is a bispecific EGF receptor-directed and MET receptor-directed antibody indicated:

- in combination with lazertinib for the first-line treatment of adult patients with locally advanced or metastatic non-small cell lung cancer (NSCLC) with epidermal growth factor receptor (EGFR) exon 19 deletions or exon 21 L858R substitution mutations, as detected by an FDA-approved test. (1, 2.2)
- in combination with carboplatin and pemetrexed for the treatment of adult patients with locally advanced or metastatic NSCLC with EGFR exon 19 deletions or exon 21 L858R substitution mutations, whose disease has progressed on or after treatment with an EGFR tyrosine kinase inhibitor. (1, 2.2)
- in combination with carboplatin and pemetrexed for the first-line treatment of adult patients with locally advanced or metastatic NSCLC with EGFR exon 20 insertion mutations, as detected by an FDA-approved test. (1, 2.2)
- as a single agent for the treatment of adult patients with locally advanced or metastatic NSCLC with EGFR exon 20 insertion mutations, as detected by an FDA-approved test, whose disease has progressed on or after platinum-based chemotherapy. (1, 2.2)

2 DOSAGE AND ADMINISTRATION

- The recommended dosage of RYBREVANT is based on baseline body weight and administered as an intravenous infusion after dilution. (2.3, 2.4)
- Administer prophylactic and concomitant medications as recommended to reduce the risk of dermatologic adverse reactions. (2.6)
- Administer via a peripheral line on Week 1 and Week 2 to reduce the risk of infusion-related reactions. (2.10)
- Administer RYBREVANT in combination with lazertinib or RYBREVANT as a single agent weekly for 5 weeks, with the initial dose as a split infusion in Week 1 on Day 1 and Day 2, then administer every 2 weeks starting at Week 7. (2.3)
- Administer RYBREVANT in combination with chemotherapy weekly for 4 weeks, with the initial dose as a split infusion in Week 1 on Day 1 and Day 2, then administer every 3 weeks starting at Week 7. (2.4)
- When administering RYBREVANT in combination with lazertinib, administer anticoagulant prophylaxis to reduce the risk of venous thromboembolic (VTE) events for the first four months of treatment. (2.7)
- Administer diluted RYBREVANT intravenously according to the infusion rates in Tables 8 and 9. (2.9, 2.10)

Body Weight (at Baseline) | Dosage | Recommended Dose
RYBREVANT in Combination with Lazertinib or RYBREVANT as a Single Agent
Less than 80 kg | Weeks 1–5 Week 7 onwards | 1,050 mg
Greater than or equal to 80 kg | Weeks 1–5 Week 7 onwards | 1,400 mg
RYBREVANT in Combination with Carboplatin and Pemetrexed
Less than 80 kg | Weeks 1–4 | 1,400 mg
Less than 80 kg | Week 7 onwards | 1,750 mg
Greater than or equal to 80 kg | Weeks 1–4 | 1,750 mg
Greater than or equal to 80 kg | Week 7 onwards | 2,100 mg

3 DOSAGE FORMS AND STRENGTHS

Injection: 350 mg/7 mL (50 mg/mL) solution in a single-dose vial (3)

4 CONTRAINDICATIONS

None. (4)

5 WARNINGS AND PRECAUTIONS

- Infusion-Related Reactions (IRR): Interrupt infusion at the first sign of IRRs. Reduce the infusion rate or permanently discontinue RYBREVANT based on severity. (2.5, 2.8, 5.1)
- Interstitial Lung Disease (ILD)/Pneumonitis: Monitor for new or worsening symptoms indicative of ILD. Immediately withhold RYBREVANT in patients with suspected ILD/pneumonitis and permanently discontinue if ILD/pneumonitis is confirmed. (2.8, 5.2)
- Venous Thromboembolic (VTE) Events with Concomitant Use with Lazertinib: Prophylactic anticoagulation is recommended for the first four months of treatment. Monitor for signs and symptoms of VTE and treat as medically appropriate. Withhold RYBREVANT and lazertinib based on severity. Once anticoagulant treatment has been initiated, resume RYBREVANT and lazertinib at the same dose at the discretion of the healthcare provider. Permanently discontinue RYBREVANT and continue lazertinib for recurrent VTE despite therapeutic anticoagulation. (2.7, 2.8, 5.3)
- Dermatologic Adverse Reactions: Can cause severe rash including toxic epidermal necrolysis (TEN) and acneiform dermatitis. At treatment initiation, prophylactic and concomitant medications are recommended. Withhold, reduce the dose, or permanently discontinue RYBREVANT based on severity. (2.6, 2.8, 5.4)
- Ocular Toxicity: Promptly refer patients with worsening eye symptoms to an ophthalmologist. Withhold, reduce the dose, or permanently discontinue RYBREVANT based on severity. (2.8, 5.5)
- Embryo-Fetal Toxicity: Can cause fetal harm. Advise females of reproductive potential of the potential risk to the fetus and to use effective contraception. (5.6, 8.1, 8.3)

6 ADVERSE REACTIONS

RYBREVANT in Combination with Lazertinib

- The most common adverse reactions (≥ 20%) were rash, nail toxicity, infusion-related reaction, musculoskeletal pain, stomatitis, edema, VTE, paresthesia, fatigue, diarrhea, constipation, COVID-19, hemorrhage, dry skin, decreased appetite, pruritus, and nausea. (6.1)
- The most common Grade 3 or 4 laboratory abnormalities (≥ 2%) were decreased albumin, decreased sodium, increased ALT, decreased potassium, decreased hemoglobin, increased AST, increased GGT, and increased magnesium. (6.1)

RYBREVANT in Combination with Carboplatin and Pemetrexed

- The most common adverse reactions (≥ 20%) were rash, nail toxicity, infusion-related reaction, fatigue, nausea, stomatitis, constipation, edema, decreased appetite, musculoskeletal pain, vomiting, and COVID-19. (6.1)
- The most common Grade 3 or 4 laboratory abnormalities (≥ 2%) were decreased neutrophils, decreased leukocytes, decreased platelets, decreased hemoglobin, decreased potassium, decreased sodium, increased alanine aminotransferase, increased gamma glutamyl transferase, and decreased albumin. (6.1)

RYBREVANT as a Single Agent

- The most common adverse reactions (≥ 20%) were rash, IRR, paronychia, musculoskeletal pain, dyspnea, nausea, fatigue, edema, stomatitis, cough, constipation, and vomiting. (6.1)
- The most common Grade 3 or 4 laboratory abnormalities (≥ 2%) were decreased lymphocytes, decreased albumin, decreased phosphate, decreased potassium, increased alkaline phosphatase, increased glucose, increased gamma-glutamyl transferase, and decreased sodium. (6.1)

To report SUSPECTED ADVERSE REACTIONS, contact Janssen Biotech, Inc. at 1-800-526-7736 or FDA at 1-800-FDA-1088 or www.fda.gov/medwatch.

8 USE IN SPECIFIC POPULATIONS

Lactation: Advise not to breastfeed. (8.2)

FULL PRESCRIBING INFORMATION

1 INDICATIONS AND USAGE

1.1 First-Line Treatment of NSCLC with EGFR Exon 19 Deletions or Exon 21 L858R Substitution Mutations

RYBREVANT, in combination with lazertinib, is indicated for the first-line treatment of adult patients with locally advanced or metastatic non-small cell lung cancer (NSCLC) with epidermal growth factor receptor (EGFR) exon 19 deletions or exon 21 L858R substitution mutations, as detected by an FDA-approved test [see Dosage and Administration (2.2)] .

1.2 Previously Treated NSCLC with EGFR Exon 19 Deletions or Exon 21 L858R Substitution Mutations

RYBREVANT, in combination with carboplatin and pemetrexed, is indicated for the treatment of adult patients with locally advanced or metastatic NSCLC with EGFR exon 19 deletions or exon 21 L858R substitution mutations, whose disease has progressed on or after treatment with an EGFR tyrosine kinase inhibitor [see Dosage and Administration (2.2)] .

1.3 First-Line Treatment of NSCLC with EGFR Exon 20 Insertion Mutations

RYBREVANT, in combination with carboplatin and pemetrexed, is indicated for the first-line treatment of adult patients with locally advanced or metastatic NSCLC with EGFR exon 20 insertion mutations, as detected by an FDA-approved test [see Dosage and Administration (2.2)] .

1.4 Previously Treated NSCLC with EGFR Exon 20 Insertion Mutations

RYBREVANT is indicated as a single agent for the treatment of adult patients with locally advanced or metastatic NSCLC with EGFR exon 20 insertion mutations, as detected by an FDA-approved test [see Dosage and Administration (2.2)] , whose disease has progressed on or after platinum-based chemotherapy.

2 DOSAGE AND ADMINISTRATION

2.1 Important Dosage Information

- To reduce the risk of infusion-related reactions, administer premedications before each RYBREVANT infusion as recommended [see Dosage and Administration (2.5)].
- To reduce the risk of infusion-related reactions, administer RYBREVANT via peripheral line for Week 1 Day 1 and 2 and Week 2 [see Dosage and Administration (2.10)].
- To reduce the risk and severity of dermatologic adverse reactions with RYBREVANT, prophylactic and concomitant medications are recommended [see Dosage and Administration (2.6)].
- To reduce the risk of venous thromboembolic (VTE) events when administering RYBREVANT in combination with lazertinib, administer anticoagulant prophylaxis for the first four months of treatment [see Dosage and Administration (2.7)].
- Administer diluted RYBREVANT intravenously according to the infusion rates in Tables 8 and 9, with the initial dose as a split infusion on Week 1 on Day 1 and Day 2 [see Dosage and Administration (2.10)].
- When administering RYBREVANT in combination with lazertinib, administer lazertinib orally any time before the RYBREVANT infusion [see Dosage and Administration (2.10)].
- When administering RYBREVANT in combination with carboplatin and pemetrexed, infuse pemetrexed first, carboplatin second, and RYBREVANT last [see Dosage and Administration (2.10)].

2.2 Patient Selection

Select patients for treatment with RYBREVANT based on the presence of a mutation as detected by an FDA-approved test.

Table 1: Patient Selection
Indication | Treatment Regimen | Source for Testing
First-Line Treatment of NSCLC with EGFR Exon 19 Deletions or Exon 21 L858R Substitution Mutations [see Indications and Usage (1.1)] | RYBREVANT in combination with lazertinib | - Tumor or plasma specimens. - Testing may be performed at any time from initial diagnosis. - Testing does not need to be repeated once EGFR mutation status has been established.
Previously treated locally advanced or metastatic NSCLC with EGFR Exon 19 deletions or Exon 21 L858R substitution mutations (progressive disease on an EGFR tyrosine kinase inhibitor) [see Indications and Usage (1.2)] | RYBREVANT in combination with carboplatin and pemetrexed | - Tumor or plasma specimens. - Testing may be performed at any time from initial diagnosis. - Testing does not need to be repeated once EGFR mutation status has been established.
First-Line Treatment of NSCLC with EGFR Exon 20 Insertion Mutations [see Indications and Usage (1.3)] | RYBREVANT in combination with carboplatin and pemetrexed | - Tumor or plasma specimens. - Testing may be performed at any time from initial diagnosis. - Testing does not need to be repeated once EGFR mutation status has been established.
Previously Treated NSCLC with EGFR Exon 20 Insertion Mutations [see Indications and Usage (1.4)] | RYBREVANT as a single agent | - Tumor or plasma specimens. - Testing may be performed at any time from initial diagnosis. - Testing does not need to be repeated once EGFR mutation status has been established.
Information on FDA approved tests is available at: http://www.fda.gov/CompanionDiagnostics.

2.3 Recommended Dosage of RYBREVANT in Combination with Lazertinib or RYBREVANT as a Single Agent - Every 2-week dosing

The recommended dosage of RYBREVANT in combination with lazertinib or RYBREVANT as a single agent, based on baseline body weight, are provided in Table 2. Administer RYBREVANT until disease progression or unacceptable toxicity.

Table 2: Recommended Dosage Schedule for RYBREVANT in Combination with Lazertinib or RYBREVANT as a Single Agent
Body weight at Baseline [Dose adjustment is not required for subsequent body weight changes.] | Recommended Dose | Dosing Schedule
Less than 80 kg | 1,050 mg | Weekly (total of 5 doses) from Weeks 1 to 5; - Week 1 - split infusion on Day 1 and Day 2 - Weeks 2 to 5 - infusion on Day 1 - Week 6 – no dose
Less than 80 kg | 1,050 mg | Every 2 weeks starting at Week 7 onwards
Greater than or equal to 80 kg | 1,400 mg | Weekly (total of 5 doses) from Weeks 1 to 5; - Week 1 - split infusion on Day 1 and Day 2 - Weeks 2 to 5 - infusion on Day 1 - Week 6 – no dose
Greater than or equal to 80 kg | 1,400 mg | Every 2 weeks starting at Week 7 onwards

RYBREVANT in Combination with Lazertinib

Order of Administration

When given in combination with lazertinib, administer RYBREVANT any time after lazertinib when given on the same day. Refer to the lazertinib prescribing information for recommended lazertinib dosing information. Administer RYBREVANT in combination with lazertinib until disease progression or unacceptable toxicity.

2.4 Recommended Dosage of RYBREVANT in Combination with Carboplatin and Pemetrexed for the Treatment of NSCLC – Every 3-week dosing

The recommended dosage of RYBREVANT, administered in combination with carboplatin and pemetrexed is based on baseline body weight is provided in Table 3.

Table 3: Recommended Dosage for RYBREVANT in Combination with Carboplatin and Pemetrexed
Body weight at Baseline [Dose adjustment is not required for subsequent body weight changes.] | Recommended Dose | Dosing Schedule
Less than 80 kg | 1,400 mg | Weekly (total of 4 doses) from Weeks 1 to 4; - Week 1 - split infusion on Day 1 and Day 2 - Weeks 2 to 4 - infusion on Day 1 - Weeks 5 and 6 – no dose
Less than 80 kg | 1,750 mg | Every 3 weeks starting at Week 7 onwards
Greater than or equal to 80 kg | 1,750 mg | Weekly (total of 4 doses) from Weeks 1 to 4; - Week 1 - split infusion on Day 1 and Day 2 - Weeks 2 to 4 - infusion on Day 1 - Weeks 5 and 6 – no dose
 | 2,100 mg | Every 3 weeks starting at Week 7 onwards

The recommended order of administration and regimen for RYBREVANT in combination with carboplatin and pemetrexed are provided in Table 4.

Table 4: Order of Administration and Regimen for RYBREVANT in Combination with Carboplatin and Pemetrexed
RYBREVANT in Combination with Carboplatin and Pemetrexed
Administer the regimen in the following order: pemetrexed first, carboplatin second, and RYBREVANT last.
Drug | Dose | Duration/Timing of Treatment
Pemetrexed | Pemetrexed 500 mg/m^2 intravenously Refer to the pemetrexed Full Prescribing Information for complete information. | Every 3 weeks, continue until disease progression or unacceptable toxicity.
Carboplatin | Carboplatin AUC 5 intravenously Refer to the carboplatin Full Prescribing Information for complete information. | Every 3 weeks for up to 12 weeks.
RYBREVANT | RYBREVANT intravenously See Table 3. | Every 3 weeks, continue until disease progression or unacceptable toxicity.

2.5 Recommended Premedications to Reduce the Risk of Infusion-Related Reactions

Administer premedications as described in Table 5 .

After prolonged dose interruptions, restart the following Week 1 Day 1 premedications upon re-initiation: intravenous dexamethasone, diphenhydramine, and acetaminophen.

Table 5: Premedications
Premedication Schedule | Medication and Frequency | Route of Administration | Dosing Window Prior to RYBREVANT Administration
Initial dose as a split infusion | Dexamethasone 8 mg (or equivalent) | Oral | 48 hours
Week 1 Day -2 | twice daily | Oral | 48 hours
Initial dose as a split infusion | Dexamethasone 8 mg (or equivalent) | Oral | 24 hours
Week 1 Day -1 | twice daily | Oral | 24 hours
Initial dose as a split infusion | Dexamethasone 8 mg (or equivalent) | Oral | One hour
Week 1 Day 1 | one dose | Oral | One hour
 | Dexamethasone 20 mg (or equivalent) one dose | Intravenous | 45 to 60 minutes
 | Diphenhydramine 25 mg to 50 mg (or equivalent) one dose | Oral | 30 to 60 minutes
 | Diphenhydramine 25 mg to 50 mg (or equivalent) one dose | Intravenous | 15 to 30 minutes
 | Acetaminophen 650 mg to 1,000 mg one dose | Oral | 30 to 60 minutes
 | Acetaminophen 650 mg to 1,000 mg one dose | Intravenous | 15 to 30 minutes
Initial dose as a split infusion | Dexamethasone 10 mg (or equivalent) | Intravenous | 45 to 60 minutes
Week 1 Day 2 | one dose | Intravenous | 45 to 60 minutes
 | Diphenhydramine 25 mg to 50 mg (or equivalent) one dose | Oral | 30 to 60 minutes
 | Diphenhydramine 25 mg to 50 mg (or equivalent) one dose | Intravenous | 15 to 30 minutes
 | Acetaminophen 650 mg to 1,000 mg one dose | Oral | 30 to 60 minutes
 | Acetaminophen 650 mg to 1,000 mg one dose | Intravenous | 15 to 30 minutes
All subsequent infusions | Diphenhydramine 25 mg to 50 mg (or equivalent) one dose | Oral | 30 to 60 minutes
All subsequent infusions | Diphenhydramine 25 mg to 50 mg (or equivalent) one dose | Intravenous | 15 to 30 minutes
All subsequent infusions | Acetaminophen 650 mg to 1,000 mg one dose | Oral | 30 to 60 minutes
All subsequent infusions | Acetaminophen 650 mg to 1,000 mg one dose | Intravenous | 15 to 30 minutes
All subsequent infusions | Optional: Dexamethasone 10 mg (or equivalent) one dose | Intravenous | 45 to 60 minutes

2.6 Prophylactic and Concomitant Medications to Reduce the Risk of Dermatologic Adverse Reactions

When initiating treatment with RYBREVANT, prophylactic and concomitant medications are recommended to reduce the risk and severity of dermatologic adverse reactions [see Warnings and Precautions (5.4)].

- Administer an oral antibiotic (doxycycline or minocycline, 100 mg orally twice daily) starting on Day 1 for the first 12 weeks of treatment.
- After completion of oral antibiotic treatment, administer antibiotic lotion to the scalp (clindamycin 1% topical once daily) for the next 9 months of treatment.
- Administer non-comedogenic skin moisturizer (ceramide-based or other formulations that provide long-lasting skin hydration and exclude drying agents) on the face and whole body (except scalp).
- Wash hands and feet with 4% chlorhexidine solution once daily.
- Limit sun exposure during and for 2 months after treatment. Advise patients to wear protective clothing and use broad-spectrum UVA/UVB sunscreen to reduce the risk of dermatologic adverse reactions.

2.7 RYBREVANT in Combination with Lazertinib: Concomitant Medications to Reduce the Risk of Venous Thromboembolic Events

When initiating treatment with RYBREVANT in combination with lazertinib, administer anticoagulant prophylaxis to reduce the risk of venous thromboembolic (VTE) events for the first four months of treatment [see Warnings and Precautions (5.3)]. If there are no signs or symptoms of VTE during the first four months of treatment, consider discontinuation of anticoagulant prophylaxis at the discretion of the healthcare provider. Refer to the lazertinib prescribing information for information about concomitant medications.

2.8 Dosage Modifications for Adverse Reactions

The recommended dose reductions for adverse reactions for RYBREVANT are listed in Table 6.

Table 6: Dose Reductions for Adverse Reactions for RYBREVANT
Dose at which the adverse reaction occurred | 1st Dose Reduction | 2nd Dose Reduction | 3rd Dose Reduction
1,050 mg | 700 mg | 350 mg | Discontinue RYBREVANT
1,400 mg | 1,050 mg | 700 mg | Discontinue RYBREVANT
1,750 mg | 1,400 mg | 1,050 mg | Discontinue RYBREVANT
2,100 mg | 1,750 mg | 1,400 mg | Discontinue RYBREVANT

The recommended dosage modifications and management for adverse reactions for RYBREVANT are provided in Table 7.

Table 7: Recommended Dosage Modifications and Management for Adverse Reactions for RYBREVANT
Adverse Reaction | Severity | Dosage Modifications
Infusion-related reactions (IRR) [see Warnings and Precautions (5.1)] | Grade 1 to 2 | - Interrupt RYBREVANT infusion if IRR is suspected and monitor patient until reaction symptoms resolve. - Resume the infusion at 50% of the infusion rate at which the reaction occurred. - If there are no additional symptoms after 30 minutes, the infusion rate may be escalated (see Tables 8 and 9). - Include corticosteroid with premedications for subsequent dose (see Table 5).
Infusion-related reactions (IRR) [see Warnings and Precautions (5.1)] | Grade 3 | - Interrupt RYBREVANT infusion and administer supportive care medications. Continuously monitor patient until reaction symptoms resolve. - Resume the infusion at 50% of the infusion rate at which the reaction occurred. - If there are no additional symptoms after 30 minutes, the infusion rate may be escalated (see Tables 8 and 9). - Include corticosteroid with premedications for subsequent dose (see Table 5). For recurrent Grade 3, permanently discontinue RYBREVANT.
Infusion-related reactions (IRR) [see Warnings and Precautions (5.1)] | Grade 4 or any Grade anaphylaxis / anaphylactic reactions | - Permanently discontinue RYBREVANT.
Interstitial Lung Disease (ILD)/pneumonitis [see Warnings and Precautions (5.2)] | Any Grade | - Withhold RYBREVANT if ILD/pneumonitis is suspected. - Permanently discontinue RYBREVANT if ILD/pneumonitis is confirmed.
Venous Thromboembolic (VTE) Events [Applies to the combination with lazertinib, see Warnings and Precautions (5.3)] | Grade 2 or 3 | - Withhold RYBREVANT and lazertinib. - Administer anticoagulant treatment as clinically indicated. - Once anticoagulant treatment has been initiated, resume RYBREVANT and lazertinib at the same dose level, at the discretion of the healthcare provider.
Venous Thromboembolic (VTE) Events [Applies to the combination with lazertinib, see Warnings and Precautions (5.3)] | Grade 4 or recurrent Grade 2 or 3 despite therapeutic level anticoagulation | - Withhold lazertinib and permanently discontinue RYBREVANT. - Administer anticoagulant treatment as clinically indicated. - Once anticoagulant treatment has been initiated, treatment can continue with lazertinib at the same dose level at the discretion of the healthcare provider.
Dermatologic Adverse Reactions (including dermatitis acneiform, pruritus, dry skin) [see Warnings and Precautions (5.4)] | Grade 1 or Grade 2 | - Initiate supportive care management as clinically indicated. - Reassess after 2 weeks; if rash does not improve, consider dose reduction.
Dermatologic Adverse Reactions (including dermatitis acneiform, pruritus, dry skin) [see Warnings and Precautions (5.4)] | Grade 3 | - Withhold RYBREVANT and initiate supportive care management as clinically indicated. - Upon recovery to ≤ Grade 2, resume RYBREVANT at reduced dose. - If no improvement within 2 weeks, permanently discontinue treatment.
Dermatologic Adverse Reactions (including dermatitis acneiform, pruritus, dry skin) [see Warnings and Precautions (5.4)] | Grade 4 or Severe bullous, blistering or exfoliating skin conditions (including toxic epidermal necrolysis (TEN)) | - Permanently discontinue RYBREVANT.
Other Adverse Reactions [see Adverse Reactions (6.1)] | Grade 3 | - Withhold RYBREVANT until recovery to ≤ Grade 1 or baseline. - Resume at the same dose if recovery occurs within 1 week. - Resume at reduced dose if recovery occurs after 1 week but within 4 weeks. - Permanently discontinue if recovery does not occur within 4 weeks.
Other Adverse Reactions [see Adverse Reactions (6.1)] | Grade 4 | - Withhold RYBREVANT until recovery to ≤ Grade 1 or baseline. - Resume at reduced dose if recovery occurs within 4 weeks. - Permanently discontinue if recovery does not occur within 4 weeks. - Permanently discontinue for recurrent Grade 4 reactions.

Recommended Dosage Modifications for Adverse Reactions for RYBREVANT in Combination with Lazertinib

When administering RYBREVANT in combination with lazertinib, if there is an adverse reaction requiring dose reduction after withholding treatment and resolution, reduce the dose of RYBREVANT first.

Refer to the lazertinib prescribing information for information about dosage modifications for lazertinib.

Recommended Dosage Modifications for Adverse Reactions for RYBREVANT in Combination with Carboplatin and Pemetrexed

When administering RYBREVANT in combination with carboplatin and pemetrexed, modify the dosage of one or more drugs. Withhold or discontinue RYBREVANT as shown in Table 7. Refer to prescribing information for carboplatin and pemetrexed for additional dosage modification information.

2.9 Preparation

Dilute and prepare RYBREVANT for intravenous infusion before administration.

- Check that the RYBREVANT solution is colorless to pale yellow. Parenteral drug products should be inspected visually for particulate matter and discoloration prior to administration, whenever solution and container permit. Do not use if discoloration or visible particles are present.
- Determine the dose required and number of RYBREVANT vials needed based on patient's baseline weight [see Dosage and Administration (2.3, 2.4)] . Each vial of RYBREVANT contains 350 mg of amivantamab-vmjw.
- Withdraw and then discard a volume of either 5% Dextrose Injection or 0.9% Sodium Chloride Injection from the 250 mL infusion bag equal to the volume of RYBREVANT to be added (i.e., discard 7 mL diluent from the infusion bag for each RYBREVANT vial). Only use infusion bags made of polyvinylchloride (PVC), polypropylene (PP), polyethylene (PE), or polyolefin blend (PP+PE).
- Withdraw 7 mL of RYBREVANT from each vial and add it to the infusion bag. The final volume in the infusion bag should be 250 mL. Discard any unused portion left in the vial.
- Gently invert the bag to mix the solution. Do not shake.
- Diluted solutions should be administered within 10 hours (including infusion time) at room temperature 15°C to 25°C (59°F to 77°F).

2.10 Administration

- Administer the diluted RYBREVANT solution [see Dosage and Administration (2.9)] by intravenous infusion using an infusion set fitted with a flow regulator and with an in-line, sterile, non-pyrogenic, low protein-binding polyethersulfone (PES) filter (pore size 0.2 micrometer).
- Administration sets must be made of either polyurethane (PU), polybutadiene (PBD), PVC, PP, or PE.
- The administration set with filter, must be primed with either 5% Dextrose Injection or 0.9% Sodium Chloride Injection prior to the initiation of each RYBREVANT infusion.
- Do not infuse RYBREVANT concomitantly in the same intravenous line with other agents.

RYBREVANT in Combination with Lazertinib or RYBREVANT as a Single Agent

- Administer RYBREVANT as a single agent infusion every 2 weeks intravenously until disease progression or unacceptable toxicity according to the infusion rates in Table 8.
- Administer RYBREVANT via a peripheral line on Week 1 and Week 2, to reduce the risk of infusion-related reactions during initial treatment [see Warnings and Precautions (5.1)].
- RYBREVANT may be administered via central line for subsequent weeks.
- For the initial infusion, prepare RYBREVANT as close to administration time as possible to allow for the possibility of extended infusion time in the event of an infusion-related reaction.
- When given in combination with lazertinib, administer RYBREVANT any time after lazertinib when given on the same day.

Table 8: Infusion Rates of RYBREVANT in Combination with Lazertinib or RYBREVANT as Single Agent
Body Weight Less Than 80 kg
Week | Dose (per 250 mL bag) | Initial Infusion Rate (mL/hr) | Subsequent Infusion Rate [In the absence of infusion-related reactions, increase the initial infusion rate to the subsequent infusion rate after 2 hours based on patient tolerance. Total infusion time is approximately 4–6 hours for day 1 and 6–8 hours for day 2. Subsequent infusion time is approximately 2 hours.] (mL/hr)
Week 1 (split dose infusion)
Week 1 Day 1 | 350 mg | 50 | 75
Week 1 Day 2 | 700 mg | 50 | 75
Week 2 | 1,050 mg | 85
Week 3 | 1,050 mg | 125
Week 4 | 1,050 mg | 125
Week 5 | 1,050 mg | 125
Week 6 | No dose
Week 7 and every 2 weeks thereafter | 1,050 mg | 125
Body Weight Greater Than or Equal to 80 kg
Week | Dose (per 250 mL bag) | Initial Infusion Rate (mL/hr) | Subsequent Infusion Rate (mL/hr)
Week 1 (split dose infusion)
Week 1 Day 1 | 350 mg | 50 | 75
Week 1 Day 2 | 1,050 mg | 35 | 50
Week 2 | 1,400 mg | 65
Week 3 | 1,400 mg | 85
Week 4 | 1,400 mg | 125
Week 5 | 1,400 mg | 125
Week 6 | No dose
Week 7 and every 2 weeks thereafter | 1,400 mg | 125

RYBREVANT in Combination with Carboplatin and Pemetrexed

- Administer RYBREVANT in combination with carboplatin and pemetrexed infusions every 3 weeks intravenously until disease progression or unacceptable toxicity according to the infusion rates in Table 9.
- Administer RYBREVANT via a peripheral line on Week 1 and Week 2 to reduce the risk of infusion-related reactions during initial treatment [see Warnings and Precautions (5.1)].
- RYBREVANT may be administered via central line for subsequent weeks.
- For the initial infusion, prepare RYBREVANT as close to administration time as possible to allow for the possibility of extended infusion time in the event of an infusion-related reaction.
- Administer the pemetrexed infusion first, carboplatin infusion second, and the RYBREVANT infusion last.

Table 9: Infusion Rates of RYBREVANT in Combination with Carboplatin and Pemetrexed for Treatment of NSCLC
Body Weight Less Than 80 kg
Week | Dose (per 250 mL bag) | Initial Infusion Rate (mL/hr) | Subsequent Infusion Rate [In the absence of infusion-related reactions, increase the initial infusion rate to the subsequent infusion rate after 2 hours based on patient tolerance. Total infusion time is approximately 4–6 hours for day 1 and 6–8 hours for day 2. Subsequent infusion time is approximately 2 hours.] (mL/hr)
Week 1 (split dose infusion)
Week 1 Day 1 | 350 mg | 50 | 75
Week 1 Day 2 | 1,050 mg | 33 | 50
Week 2 | 1,400 mg | 65
Week 3 | 1,400 mg | 85
Week 4 | 1,400 mg | 125
Weeks 5 and 6 |  | No dose
Week 7 and every 3 weeks thereafter | 1,750 mg | 125
Body Weight Greater Than or Equal to 80 kg
Week | Dose (per 250 mL bag) | Initial Infusion Rate (mL/hr) | Subsequent Infusion Rate (mL/hr)
Week 1 (split dose infusion)
Week 1 Day 1 | 350 mg | 50 | 75
Week 1 Day 2 | 1,400 mg | 25 | 50
Week 2 | 1,750 mg | 65
Week 3 | 1,750 mg | 85
Week 4 | 1,750 mg | 125
Week 5 and 6 |  | No dose
Week 7 and every 3 weeks thereafter | 2,100 mg | 125

3 DOSAGE FORMS AND STRENGTHS

Injection: 350 mg/7 mL (50 mg/mL) colorless to pale yellow solution in a single-dose vial.

4 CONTRAINDICATIONS

None.

5 WARNINGS AND PRECAUTIONS

5.1 Infusion-Related Reactions

RYBREVANT can cause infusion-related reactions (IRR) including anaphylaxis; signs and symptoms of IRR include dyspnea, flushing, fever, chills, nausea, chest discomfort, hypotension, and vomiting. The median time to IRR onset is approximately 1 hour.

RYBREVANT with Lazertinib

RYBREVANT in combination with lazertinib can cause infusion-related reactions. In MARIPOSA, [see Adverse Reactions (6.1)] , IRRs occurred in 63% of patients treated with RYBREVANT in combination with lazertinib, including Grade 3 in 5% and Grade 4 in 1% of patients. The incidence of infusion modifications due to IRR was 54%, and IRRs leading to dose reduction of RYBREVANT occurred in 0.7% of patients. Infusion-related reactions leading to permanent discontinuation of RYBREVANT occurred in 4.5% of patients receiving RYBREVANT in combination with lazertinib.

RYBREVANT with Carboplatin and Pemetrexed

Based on the pooled safety population [see Adverse Reactions (6.1)] , IRR occurred in 50% of patients treated with RYBREVANT in combination with carboplatin and pemetrexed, including Grade 3 (3.2%) adverse reactions. The incidence of infusion modifications due to IRR was 46%, and 2.8% of patients permanently discontinued RYBREVANT due to IRR.

RYBREVANT as a Single Agent

In CHRYSALIS, [see Adverse Reactions (6.1)], IRR occurred in 66% of patients treated with RYBREVANT as a single agent. Among patients receiving treatment on Week 1 Day 1, 65% experienced an IRR, while the incidence of IRR was 3.4% with the Day 2 infusion, 0.4% with the Week 2 infusion, and cumulatively 1.1% with subsequent infusions. Of the reported IRRs, 97% were Grade 1–2, 2.2% were Grade 3, and 0.4% were Grade 4. The median time to onset was 1 hour (range 0.1 to 18 hours) after start of infusion. The incidence of infusion modifications due to IRR was 62%, and 1.3% of patients permanently discontinued RYBREVANT due to IRR.

Premedicate with antihistamines, antipyretics, and glucocorticoids and infuse RYBREVANT as recommended [see Dosage and Administration (2.5)] . Administer RYBREVANT via a peripheral line on Week 1 and Week 2 to reduce the risk of infusion-related reactions [see Dosage and Administration (2.10)] .

Monitor patients for signs and symptoms of infusion reactions during RYBREVANT infusion in a setting where cardiopulmonary resuscitation medication and equipment are available. Interrupt infusion if IRR is suspected. Reduce the infusion rate or permanently discontinue RYBREVANT based on severity [see Dosage and Administration (2.8)]. If an anaphylactic reaction occurs, permanently discontinue RYBREVANT.

5.2 Interstitial Lung Disease/Pneumonitis

RYBREVANT can cause severe and fatal interstitial lung disease (ILD)/pneumonitis.

RYBREVANT with Lazertinib

In MARIPOSA [see Adverse Reactions (6.1)] , ILD/pneumonitis occurred in 3.1% of patients treated with RYBREVANT in combination with lazertinib, including Grade 3 in 1% and Grade 4 in 0.2% of patients. There was one fatal case of ILD/pneumonitis and 2.9% of patients permanently discontinued RYBREVANT and lazertinib due to ILD/pneumonitis [see Adverse Reactions (6.1)].

RYBREVANT with Carboplatin and Pemetrexed

Based on the pooled safety population [see Adverse Reactions (6.1)], ILD/pneumonitis occurred in 2.1% treated with RYBREVANT in combination with carboplatin and pemetrexed with 1.8% of patients experiencing Grade 3 ILD/pneumonitis. 2.1% discontinued RYBREVANT due to ILD/pneumonitis.

RYBREVANT as a Single Agent

In CHRYSALIS, [see Adverse Reactions (6.1)] , ILD/pneumonitis occurred in 3.3% of patients treated with RYBREVANT as a single agent, with 0.7% of patients experiencing Grade 3 ILD/pneumonitis. Three patients (1%) permanently discontinued RYBREVANT due to ILD/pneumonitis.

Monitor patients for new or worsening symptoms indicative of ILD/pneumonitis (e.g., dyspnea, cough, fever). Immediately withhold RYBREVANT in patients with suspected ILD/pneumonitis and permanently discontinue if ILD/pneumonitis is confirmed [see Dosage and Administration (2.8)] .

5.3 Venous Thromboembolic (VTE) Events with Concomitant Use of RYBREVANT and Lazertinib

RYBREVANT in combination with lazertinib can cause serious and fatal venous thromboembolic (VTE) events, including deep vein thrombosis and pulmonary embolism. The majority of these events occurred during the first four months of treatment [see Adverse Reactions (6.1)] .

In MARIPOSA [see Adverse Reactions (6.1)], VTEs occurred in 36% of patients receiving RYBREVANT in combination with lazertinib, including Grade 3 in 10% and Grade 4 in 0.5% of patients. On-study VTEs occurred in 1.2% of patients (n=5) while receiving anticoagulation therapy. There were two fatal cases of VTE (0.5%), 9% of patients had VTE leading to dose interruptions of RYBREVANT, 1% of patients had VTE leading to dose reductions of RYBREVANT, and 3.1% of patients had VTE leading to permanent discontinuation of RYBREVANT. The median time to onset of VTEs was 84 days (range: 6 to 777). Administer prophylactic anticoagulation for the first four months of treatment [see Dosage and Administration (2.7)]. The use of Vitamin K antagonists is not recommended. Monitor for signs and symptoms of VTE events and treat as medically appropriate.

Withhold RYBREVANT and lazertinib based on severity [see Dosage and Administration (2.8)] . Once anticoagulant treatment has been initiated, resume RYBREVANT and lazertinib at the same dose level at the discretion of the healthcare provider. In the event of VTE recurrence despite therapeutic anticoagulation, permanently discontinue RYBREVANT. Treatment can continue with lazertinib at the same dose level at the discretion of the healthcare provider [see Dosage and Administration (2.8)]. Refer to the lazertinib prescribing information for recommended lazertinib dosage modification.

5.4 Dermatologic Adverse Reactions

RYBREVANT can cause severe rash including toxic epidermal necrolysis (TEN), dermatitis acneiform, pruritus, and dry skin.

RYBREVANT with Lazertinib

In MARIPOSA, [see Adverse Reactions (6.1)] , rash occurred in 86% of patients treated with RYBREVANT in combination with lazertinib, including Grade 3 in 26% of patients. The median time to onset of rash was 14 days (range: 1 to 556 days). Rash leading to dose interruptions of RYBREVANT occurred in 37% of patients, rash leading to dose reductions of RYBREVANT occurred in 23% of patients, and rash leading to permanent discontinuation of RYBREVANT occurred in 5% of patients.

RYBREVANT with Carboplatin and Pemetrexed

Based on the pooled safety population [see Adverse Reactions (6.1)] , rash occurred in 82% of patients treated with RYBREVANT in combination with carboplatin and pemetrexed, including Grade 3 (15%) adverse reactions. Rash leading to dose reductions occurred in 14% of patients, and 2.5% permanently discontinued RYBREVANT and 3.1% discontinued pemetrexed.

RYBREVANT as a Single Agent

In CHRYSALIS, [see Adverse Reactions (6.1)] , rash occurred in 74% of patients treated with RYBREVANT as a single agent, including Grade 3 rash in 3.3% of patients. The median time to onset of rash was 14 days (range: 1 to 276 days). Rash leading to dose reduction occurred in 5% of patients, and RYBREVANT was permanently discontinued due to rash in 0.7% of patients [see Adverse Reactions (6.1)].

Toxic epidermal necrolysis (TEN) occurred in one patient (0.3%) treated with RYBREVANT as a single agent.

When initiating treatment with RYBREVANT, prophylactic and concomitant medications are recommended to reduce the risk and severity of dermatologic adverse reactions [see Dosage and Administration (2.6)]. Instruct patients to limit sun exposure during and for 2 months after treatment with RYBREVANT. Advise patients to wear protective clothing and use broad-spectrum UVA/UVB sunscreen.

If skin reactions develop, administer supportive care including topical corticosteroids and topical and/or oral antibiotics. For Grade 3 reactions, add oral steroids and consider dermatologic consultation. Promptly refer patients presenting with severe rash, atypical appearance or distribution, or lack of improvement within 2 weeks to a dermatologist. Withhold, reduce the dose, or permanently discontinue RYBREVANT based on severity [see Dosage and Administration (2.8)].

5.5 Ocular Toxicity

RYBREVANT can cause ocular toxicity including keratitis, blepharitis, dry eye symptoms, conjunctival redness, blurred vision, visual impairment, ocular itching, eye pruritus, and uveitis.

RYBREVANT with Lazertinib

In MARIPOSA [see Adverse Reactions (6.1)] , ocular toxicity occurred in 16% of patients treated with RYBREVANT in combination with lazertinib, including Grade 3 or 4 ocular toxicity in 0.7% of patients. Withhold, reduce the dose, or permanently discontinue RYBREVANT and continue lazertinib based on severity [see Dosage and Administration (2.8)] .

RYBREVANT with Carboplatin and Pemetrexed

Based on the pooled safety population [see Adverse Reactions (6.1)], ocular toxicity occurred in 16% of patients treated with RYBREVANT in combination with carboplatin and pemetrexed. All events were Grade 1 or 2.

RYBREVANT as a Single Agent

In CHRYSALIS, [see Adverse Reactions (6.1)] , keratitis occurred in 0.7% and uveitis occurred in 0.3% of patients treated with RYBREVANT. All events were Grade 1–2.

Promptly refer patients with new or worsening eye symptoms to an ophthalmologist. Withhold, reduce the dose, or permanently discontinue RYBREVANT based on severity [see Dosage and Administration (2.8)] .

5.6 Embryo-Fetal Toxicity

Based on its mechanism of action and findings from animal models, RYBREVANT can cause fetal harm when administered to a pregnant woman. Administration of other EGFR inhibitor molecules to pregnant animals has resulted in an increased incidence of impairment of embryo-fetal development, embryo lethality, and abortion. Advise females of reproductive potential of the potential risk to the fetus. Advise female patients of reproductive potential to use effective contraception during treatment and for 3 months after the last dose of RYBREVANT. [see Use in Specific Populations (8.1, 8.3)] .

6 ADVERSE REACTIONS

The following adverse reactions are discussed elsewhere in the labeling:

- Infusion-Related Reactions [see Warnings and Precautions (5.1)]
- Interstitial Lung Disease/Pneumonitis [see Warnings and Precautions (5.2)]
- Venous Thromboembolic Events [see Warnings and Precautions (5.3)]
- Dermatologic Adverse Reactions [see Warnings and Precautions (5.4)]
- Ocular Toxicity [see Warnings and Precautions (5.5)]

6.1 Clinical Trials Experience

Because clinical trials are conducted under widely varying conditions, adverse reaction rates observed in the clinical trials of a drug cannot be directly compared to rates in the clinical trials of another drug and may not reflect the rates observed in practice.

RYBREVANT in Combination with Lazertinib

The data described in the WARNINGS AND PRECAUTIONS reflect exposure to RYBREVANT in combination with lazertinib in the MARIPOSA study in 421 patients with previously untreated locally advanced or metastatic NSCLC whose tumors have EGFR exon 19 deletions or exon 21 L858R substitution mutations [see Clinical Studies (14.1)] . Patients received RYBREVANT intravenously at 1,050 mg (for patients < 80 kg) or 1,400 mg (for patients ≥ 80 kg) once weekly for 4 weeks, then every 2 weeks thereafter starting at week 5 in combination with lazertinib, 240 mg orally once daily, until disease progression or unacceptable toxicity. Among 421 patients who received RYBREVANT in combination with lazertinib, 73% were exposed for 6 months or longer and 59% were exposed for greater than one year. The most common adverse reactions (≥ 20%) were rash, nail toxicity, infusion-related reaction, edema, musculoskeletal pain, stomatitis, VTE, paresthesia, fatigue, diarrhea, constipation, COVID-19, dry skin, hemorrhage, decreased appetite, pruritus, and nausea. The most common Grade 3 or 4 laboratory abnormalities (≥ 2%) were decreased albumin, increased ALT, decreased sodium, decreased hemoglobin, increased AST, increased GGT and increased magnesium.

RYBREVANT in Combination with Carboplatin and Pemetrexed

The pooled safety population described in the WARNINGS AND PRECAUTIONS also reflect exposure to RYBREVANT in combination with carboplatin and pemetrexed in 281 patients in two studies:

- MARIPOSA-2 [see Clinical Studies (14.2)] in 130 patients with previously treated locally advanced or metastatic NSCLC with EGFR exon 19 deletions or exon 21 L858R substitution mutations whose disease has progressed on or after treatment with osimertinib.
- PAPILLON [see Clinical Studies (14.3)] in 151 patients with previously untreated, locally advanced or metastatic NSCLC with EGFR exon 20 insertion mutations.

Patients received RYBREVANT intravenously at 1,400 mg (for patients < 80 kg) or 1,750 mg (for patients ≥ 80 kg) once weekly through 4 weeks, then every 3 weeks with a dose of 1,750 mg (for patients < 80 kg) or 2,100 mg (for patients ≥ 80 kg) starting at Week 7 until disease progression or unacceptable toxicity, in combination with carboplatin at area under the curve AUC 5 once every 3 weeks, for up to 12 weeks, and pemetrexed at 500 mg/m^2 once every 3 weeks until disease progression or unacceptable toxicity. Among 281 patients who received RYBREVANT in combination with carboplatin and pemetrexed, 65% were exposed for 6 months or longer and 24% were exposed for greater than one year. In the safety population, the most common (≥ 20%) adverse reactions were rash, nail toxicity, infusion-related reaction, fatigue, nausea, stomatitis, constipation, edema, decreased appetite, musculoskeletal pain, vomiting, and COVID-19. The most common Grade 3 to 4 laboratory abnormalities (≥ 2%) were decreased neutrophils, decreased leukocytes, decreased platelets, decreased hemoglobin, decreased potassium, decreased sodium, increased alanine aminotransferase, increased gamma-glutamyl transferase, and decreased albumin.

RYBREVANT as a Single Agent

The data in the WARNINGS AND PRECAUTIONS also reflect exposure to RYBREVANT as a single agent in CHRYSALIS [see Clinical Studies (14.4)] in 302 patients with locally advanced or metastatic NSCLC. Patients received RYBREVANT at 1,050 mg (for patient baseline body weight < 80 kg) or 1,400 mg (for patient baseline body weight ≥ 80 kg) once weekly for 4 weeks, then every 2 weeks thereafter until disease progression or unacceptable toxicity. Among 302 patients who received RYBREVANT as a single agent, 36% were exposed for 6 months or longer and 12% were exposed for greater than one year. In the safety population, the most common (≥ 20%) adverse reactions were rash, infusion-related reaction, paronychia, musculoskeletal pain, dyspnea, nausea, edema, cough, fatigue, stomatitis, constipation, vomiting and pruritus. The most common Grade 3 to 4 laboratory abnormalities (≥ 2%) were increased gamma glutamyl transference, decreased sodium, decreased potassium and increased alkaline phosphatase.

First-line Treatment of NSCLC with Exon 19 deletions or Exon 21 L858R substitution mutations

The safety data described below reflect exposure to RYBREVANT in combination with lazertinib in 421 previously untreated patients with locally advanced or metastatic NSCLC whose tumors have EGFR exon 19 deletions or exon 21 L858R substitution mutation in the MARIPOSA [see Clinical Studies (14.1)]. Patients received RYBREVANT intravenously at 1,050 mg (for patients < 80 kg) or 1,400 mg (for patients ≥ 80 kg) once weekly for 4 weeks, then every 2 weeks thereafter starting at week 5 in combination with lazertinib, 240 mg orally once daily. Among the 421 patients who received RYBREVANT in combination with lazertinib, 73% were exposed to RYBREVANT for ≥ 6 months and 59% were exposed to RYBREVANT for > 1 year.

The median age of patients who received RYBREVANT in combination with lazertinib was 64 years (range: 25 to 88); 64% were female; 59% were Asian, 38% were White, 1.7% were American Indian or Alaska Native, 0.7% were Black or African American, 1% were of unknown or other races; and 13% were Hispanic or Latino, 67% had Eastern Cooperative Oncology Group (ECOG) performance status (PS) of 1, 33% had ECOG PS of 0, 60% had EGFR exon 19 deletions, and 40% had EGFR exon 21 L858R substitution mutations.

Serious adverse reactions occurred in 49% of patients who received RYBREVANT in combination with lazertinib. Serious adverse reactions occurring in ≥ 2% of patients included VTE (11%), pneumonia (4%), rash, and ILD/pneumonitis (2.9% each), COVID-19 (2.4%), pleural effusion and infusion-related reaction (2.1% each). Fatal adverse reactions occurred in 7% of patients who received RYBREVANT in combination with lazertinib due to death not otherwise specified (1.2%); sepsis and respiratory failure (1% each); pneumonia, myocardial infarction and sudden death (0.7% each); cerebral infarction, pulmonary embolism (PE), and COVID-19 infection (0.5% each); and ILD/pneumonitis, acute respiratory distress syndrome (ARDS), and cardiopulmonary arrest (0.2% each).

Permanent discontinuation of RYBREVANT due to an adverse reaction occurred in 34% of patients. Adverse reactions which resulted in permanent discontinuation in ≥ 1% of patients included rash, infusion-related reactions, nail toxicity, VTE, ILD/pneumonitis, pneumonia, edema, hypoalbuminemia, fatigue, paresthesia and dyspnea.

Dosage interruption of RYBREVANT due to an adverse reaction occurred in 88% of patients. Adverse reactions which required dosage interruption in ≥ 5% of patients were infusion-related reactions, rash, nail toxicity, COVID-19, VTE, increased ALT, edema, and hypoalbuminemia.

Dose reductions of RYBREVANT due to an adverse reaction occurred in 46% of patients. Adverse reactions requiring dose reductions in ≥ 5% of patients were rash and nail toxicity.

The most common adverse reactions (≥ 20%) were rash, nail toxicity, infusion-related reaction, musculoskeletal pain, stomatitis, edema, VTE, paresthesia, fatigue, diarrhea, constipation, COVID-19, hemorrhage, dry skin, decreased appetite, pruritus, and nausea. The most common Grade 3 or 4 laboratory abnormalities (≥ 2%) were decreased albumin, decreased sodium, increased ALT, decreased potassium, decreased hemoglobin, increased AST, increased GGT, and increased magnesium.

Table 10 summarizes the adverse reactions (≥ 10%) in MARIPOSA.

Table 10: Adverse Reactions (≥ 10%) in Patients with NSCLC with Exon 19 Deletion or Exon 21 L858R Substitution Mutations in MARIPOSA
Adverse Reaction | RYBREVANT in combination with lazertinib (N=421) |  | Osimertinib (N=428)
Adverse Reaction | All Grades (%) | Grade 3 or 4 (%) | All Grades (%) | Grade 3 or 4 (%)
Skin and subcutaneous tissue disorders
Rash [Grouped terms] | 86 | 26 | 48 | 1.2
Nail toxicity | 71 | 11 | 34 | 0.7
Dry skin | 25 | 1 | 18 | 0.2
Pruritus | 24 | 0.5 | 17 | 0.2
Injury, poisoning and procedural complications
Infusion-related reaction [Applicable for RYBREVANT only] | 63 | 6 | 0 | 0
Musculoskeletal and connective tissue disorders
Musculoskeletal pain | 47 | 2.1 | 39 | 1.9
Gastrointestinal disorders
Stomatitis | 43 | 2.4 | 27 | 0.5
Diarrhea | 31 | 2.6 | 45 | 0.9
Constipation | 29 | 0 | 13 | 0
Nausea | 21 | 1.2 | 14 | 0.2
Vomiting | 12 | 0.5 | 5 | 0
Abdominal pain | 11 | 0 | 10 | 0
Hemorrhoids | 10 | 0.2 | 2.1 | 0.2
General disorders and administration site conditions
Edema | 43 | 2.6 | 8 | 0
Fatigue | 32 | 3.8 | 20 | 1.9
Pyrexia | 12 | 0 | 9 | 0
Vascular disorders
Venous thromboembolism | 36 | 11 | 8 | 2.8
Hemorrhage | 25 | 1 | 13 | 1.2
Nervous system disorders
Paresthesia | 35 | 1.7 | 10 | 0.2
Dizziness | 14 | 0 | 10 | 0
Headache | 13 | 0.2 | 13 | 0
Infections and infestations
COVID-19 | 26 | 1.7 | 24 | 1.4
Conjunctivitis | 11 | 0.2 | 1.6 | 0
Metabolism and nutrition disorders
Decreased appetite | 24 | 1 | 18 | 1.4
Respiratory, thoracic and mediastinal disorders
Cough | 19 | 0 | 23 | 0
Dyspnea | 14 | 1.7 | 17 | 3.5
Eye disorders
Ocular toxicity | 16 | 0.7 | 7 | 0
Psychiatric disorders
Insomnia | 10 | 0 | 11 | 0

Clinically relevant adverse reactions in < 10% of patients who received RYBREVANT in combination with lazertinib included skin ulcer and ILD/pneumonitis.

Table 11 summarizes the laboratory abnormalities in MARIPOSA.

Table 11: Select Laboratory Abnormalities (≥ 20%) That Worsened from Baseline in Patients with NSCLC with EGFR Exon 19 Deletion or Exon 21 L858R Substitution Mutations in MARIPOSA [The denominator used to calculate the rate is the number of patients with a baseline value and at least one post-treatment value for the specific lab test.]
 | RYBREVANT in combination with lazertinib (N=421) |  | Osimertinib (N=428)
Laboratory Abnormality | All Grades (%) | Grade 3 or 4 (%) | All Grades (%) | Grade 3 or 4 (%)
Chemistry
Decreased albumin | 89 | 8 | 22 | 0.2
Increased ALT | 65 | 7 | 29 | 2.6
Increased AST | 52 | 3.8 | 36 | 1.9
Increased alkaline phosphatase | 45 | 0.5 | 15 | 0.5
Decreased calcium (corrected) | 41 | 1.4 | 27 | 0.7
Increased GGT | 39 | 2.6 | 24 | 1.9
Decreased sodium | 38 | 7 | 35 | 5
Decreased potassium | 30 | 5 | 15 | 1.2
Increased creatinine | 26 | 0.7 | 35 | 0.7
Decreased magnesium | 25 | 0.7 | 10 | 0.2
Increased magnesium | 12 | 2.6 | 20 | 4.8
Hematology
Decreased platelet count | 52 | 0.7 | 57 | 1.4
Decreased hemoglobin | 47 | 3.8 | 56 | 1.9
Decreased white blood cell | 38 | 1 | 66 | 0.7
Decreased neutrophils | 15 | 1.4 | 33 | 1.4

Previously Treated Non-Small Cell Lung Cancer (NSCLC) with EGFR Exon 19 Deletions or Exon 21 L858R Substitution Mutations

The safety data described below reflect exposure to RYBREVANT in combination with carboplatin and pemetrexed was evaluated in MARIPOSA-2 [see Clinical Studies (14.2)]. Eligible patients had locally advanced or metastatic NSCLC with EGFR exon 19 deletions or exon 21 L858R substitution mutations with progressive disease on or after treatment with osimertinib . Patients with asymptomatic or previously treated and stable intracranial metastases were eligible. Patients received RYBREVANT intravenously at 1,400 mg (for patients < 80 kg) or 1,750 mg (for patients ≥ 80 kg) once weekly through 4 weeks, then every 3 weeks with a dose of 1,750 mg (for patients < 80 kg) or 2,100 mg (for patients ≥ 80 kg) starting at Week 7 until disease progression or unacceptable toxicity, in combination with carboplatin at area under the curve AUC 5 once every 3 weeks, for up to 12 weeks, and pemetrexed at 500 mg/m^2 once every 3 weeks until disease progression or unacceptable toxicity. Among patients who received RYBREVANT (n=130), 52% were exposed for 6 months or longer and 7% were exposed for greater than one year. The median treatment duration was 6.3 months (range: 0 to 14.7 months).

The median age was 62 years (range: 36 to 84 years); 62% were female; 48% were Asian, 46% were White, 2.3% Black or African American, 1.5% race not reported, 1.5% race unknown, 0.8% Alaska native; 7% were Hispanic or Latino; and 87% had baseline body weight < 80 kg.

Serious adverse reactions occurred in 32% of patients who received RYBREVANT in combination with carboplatin and pemetrexed. Serious adverse reactions in > 2% of patients included dyspnea (3.1%), thrombocytopenia (3.1%), sepsis (2.3%), and pulmonary embolism (2.3%). Fatal adverse reactions occurred in 2.3% of patients who received RYBREVANT in combination with carboplatin and pemetrexed; these included respiratory failure, sepsis, and ventricular fibrillation (0.8% each).

Permanent discontinuation of RYBREVANT due to adverse reactions occurred in 11% of patients. The most frequent adverse reactions leading to discontinuation of RYBREVANT in ≥ 5% of patients were infusion-related reactions.

Dose interruptions of RYBREVANT due to an adverse reaction occurred in 60% of patients. Infusion-related reactions (IRR) requiring infusion interruptions occurred in 52% of patients. Adverse reactions requiring dose interruption in ≥ 5% of patients included infusion-related reaction, rash and fatigue.

Dose reductions of RYBREVANT due to an adverse reaction occurred in 17% of patients. Adverse reactions requiring dose reductions in ≥ 2% of patients included rash.

The most common adverse reactions ≥ 20% were rash, infusion-related reactions, fatigue, nail toxicity, nausea, constipation, edema, stomatitis, decreased appetite, musculoskeletal pain, vomiting, and COVID-19.

Table 12 summarizes the adverse reactions in MARIPOSA-2.

Table 12: Adverse Reactions (≥ 10%) in Previously Treated Patients with NSCLC with EGFR Exon 19 Deletions or Exon 21 L858R Substitution Mutations Treated with RYBREVANT in Combination with Carboplatin and Pemetrexed in MARIPOSA-2
Adverse Reaction | RYBREVANT + Carboplatin + Pemetrexed |  | Carboplatin + Pemetrexed
 | (N=130) |  | (N=243)
 | All Grades (%) | Grade 3 or 4 (%) | All Grades (%) | Grade 3 or 4 (%)
Skin and subcutaneous tissue disorders
Rash [Grouped term] | 72 | 11 | 12 | 0
Nail toxicity | 45 | 2.3 | 0.4 | 0
Pruritus | 15 | 0 | 7 | 0
Dry skin | 15 | 0 | 2.5 | 0
General disorders and administration site conditions
Infusion-related reaction | 59 | 5.4 | 0.4 | 0
Fatigue | 51 | 3.8 | 35 | 3.7
Edema | 36 | 1.5 | 11 | 0.4
Pyrexia | 12 | 0 | 10 | 0
Gastrointestinal disorders
Nausea | 45 | 0.8 | 37 | 0.8
Constipation | 39 | 0.8 | 30 | 0
Stomatitis | 35 | 2.3 | 11 | 0
Vomiting | 25 | 0.8 | 17 | 0.4
Diarrhea | 15 | 1.5 | 7 | 0.8
Metabolism and nutrition disorders
Decreased appetite | 31 | 0 | 21 | 1.2
Musculoskeletal and connective tissue disorders
Musculoskeletal pain | 30 | 3.1 | 19 | 0.8
Infections and infestations
COVID-19 | 21 | 1.5 | 10 | 0
Eye disorders
Ocular toxicity | 17 | 0 | 3.7 | 0
Vascular disorders
Hemorrhage | 14 | 0.8 | 4.9 | 0
Venous Thromboembolism (VTE) | 10 | 2.3 | 4.5 | 2.9
Respiratory, thoracic and mediastinal disorders
Cough | 14 | 0 | 16 | 0.4
Dyspnea | 13 | 1.5 | 8 | 1.2

Clinically relevant adverse reactions in < 10% of patients who received RYBREVANT in combination with carboplatin and pemetrexed include: abdominal pain, hemorrhoids, dizziness, visual impairment, trichomegaly, keratitis, interstitial lung disease, and skin ulcer.

Table 13 summarizes the laboratory abnormalities in MARIPOSA-2.

Table 13: Select Laboratory Abnormalities (≥ 20%) That Worsened from Baseline in Patients with NSCLC with EGFR Exon 19 Deletions or Exon 21 L858R Substitution Mutations Treated with RYBREVANT in Combination with Carboplatin and Pemetrexed in MARIPOSA-2
 | RYBREVANT + Carboplatin + Pemetrexed (N=130) |  | Carboplatin + Pemetrexed (N=243)
Laboratory Abnormality | All Grades (%) | Grade 3 or 4 (%) | All Grades (%) | Grade 3 or 4 (%)
Hematology
Decreased white blood cells | 91 | 42 | 85 | 19
Decreased neutrophils | 74 | 49 | 64 | 25
Decreased platelets | 74 | 17 | 58 | 9
Decreased hemoglobin | 71 | 12 | 77 | 9
Decreased lymphocytes | 69 | 28 | 58 | 18
Chemistry
Decreased albumin | 73 | 3.8 | 26 | 0.4
Decreased sodium | 49 | 11 | 30 | 6
Increased aspartate aminotransferase | 47 | 0.8 | 52 | 0.9
Increased alkaline phosphatase | 42 | 0 | 29 | 0.4
Increased alanine aminotransferase | 39 | 3.9 | 56 | 6
Decreased magnesium | 38 | 0.8 | 17 | 0.4
Decreased potassium | 37 | 11 | 12 | 3.4
Increased gamma-glutamyl transferase | 30 | 3.1 | 41 | 1.3
Decreased calcium (corrected) | 25 | 0 | 11 | 0.9

First-line Treatment of Non-Small Cell Lung Cancer (NSCLC) with Exon 20 Insertion Mutations

The safety data described below reflect exposure to RYBREVANT in combination with carboplatin and pemetrexed at the recommended dosage in the PAPILLON trial [see Clinical Studies (14.3)] in 151 patients with locally advanced or metastatic NSCLC with EGFR exon 20 insertion mutations. Among patients who received RYBREVANT in combination with carboplatin and pemetrexed the median exposure was 9.7 months (range: 0.0 to 26.9 months). In patients that received carboplatin and pemetrexed alone, the median exposure was 6.7 months (range 0.0 to 25.3).

The median age was 61 years (range: 27 to 86 years); 56% were female; 64% were Asian, 32% were White, 1.3% were Black or African American, race was not reported in 1.3% of patients; 89% were not Hispanic or Latino; 86% had baseline body weight < 80 kg.

Serious adverse reactions occurred in 37% of patients who received RYBREVANT in combination with carboplatin and pemetrexed. Serious adverse reactions in ≥ 2% of patients included rash, pneumonia, interstitial lung disease (ILD), pulmonary embolism, vomiting, and COVID-19. Fatal adverse reactions occurred in 7 patients (4.6%) due to pneumonia, cerebrovascular accident, cardio-respiratory arrest, COVID-19, sepsis, and death not otherwise specified.

Permanent discontinuation of RYBREVANT due to an adverse reaction occurred in 11% of patients. Adverse reactions resulting in permanent discontinuation of RYBREVANT in ≥ 1% of patients were rash and ILD.

Dose interruptions of RYBREVANT due to an adverse reaction occurred in 64% of patients. Infusion-related reactions (IRR) requiring infusion interruptions occurred in 38% of patients. Adverse reactions requiring dose interruption in ≥ 5% of patients included rash and nail toxicity.

Dose reductions of RYBREVANT due to an adverse reaction occurred in 36% of patients. Adverse reactions requiring dose reductions in ≥ 5% of patients included rash and nail toxicity.

The most common adverse reactions (≥ 20%) were rash, nail toxicity, stomatitis, infusion-related reaction, fatigue, edema, constipation, decreased appetite, nausea, COVID-19, diarrhea, and vomiting. The most common Grade 3 to 4 laboratory abnormalities (≥ 2%) were decreased albumin, increased alanine aminotransferase, increased gamma-glutamyl transferase, decreased sodium, decreased potassium, decreased magnesium, and decreases in white blood cells, hemoglobin, neutrophils, platelets, and lymphocytes.

Table 14 summarizes the adverse reactions in PAPILLON.

Table 14: Adverse Reactions (≥ 10%) in Patients with Metastatic NSCLC with Exon 20 Insertion Mutations Who Received RYBREVANT in Combination with Carboplatin and Pemetrexed in PAPILLON
 | RYBREVANT in Combination with Carboplatin and Pemetrexed (n=151) |  | Carboplatin and Pemetrexed (n=155)
Adverse Reaction [Adverse reactions were graded using CTCAE version 5.0.] | All Grades (%) | Grade 3 or 4 (%) | All Grades (%) | Grade 3 or 4 (%)
Skin and subcutaneous tissue disorders
Rash [Grouped Term] | 90 | 19 | 19 | 0
Nail toxicity | 62 | 7 | 3 | 0
Dry skin | 17 | 0 | 6 | 0
Gastrointestinal disorders
Stomatitis | 43 | 4 | 11 | 0
Constipation | 40 | 0 | 30 | 0.7
Nausea | 36 | 0.7 | 42 | 0
Vomiting | 21 | 3.3 | 19 | 0.7
Diarrhea | 21 | 3 | 13 | 1.3
Hemorrhoids | 12 | 1 | 1.3 | 0
Abdominal pain | 11 | 0.7 | 8 | 0
General disorders and administration site conditions
Infusion-related reaction | 42 | 1.3 | 1.3 | 0
Fatigue | 42 | 6 | 45 | 3.9
Edema | 40 | 1.3 | 19 | 0
Pyrexia | 17 | 0 | 6 | 0
Metabolism and nutrition disorders
Decreased appetite | 36 | 2.6 | 28 | 1.3
Infections and infestations
COVID-19 | 24 | 2 | 14 | 0.6
Pneumonia | 13 | 5 | 6 | 1.9
Vascular disorders
Hemorrhage | 18 | 0.7 | 11 | 1.9
Respiratory, thoracic, and mediastinal disorders
Cough | 17 | 0 | 16 | 0
Dyspnea | 11 | 1.3 | 16 | 3.2
Investigations
Weight decreased | 14 | 0.7 | 8 | 0
Nervous system disorders
Dizziness | 11 | 0 | 12 | 0
Psychiatric disorders
Insomnia | 11 | 0 | 13 | 0

Clinically relevant adverse reactions in < 10% of patients who received RYBREVANT in combination with carboplatin and pemetrexed included pulmonary embolism, deep vein thrombosis, skin ulcer, conjunctivitis, and interstitial lung disease (ILD)/pneumonitis.

Table 15 summarizes the laboratory abnormalities in PAPILLON.

Table 15: Select Laboratory Abnormalities (≥ 20%) That Worsened from Baseline in Patients with Metastatic NSCLC with EGFR Exon 20 Insertion Mutations Who Received RYBREVANT in Combination with Carboplatin and Pemetrexed in PAPILLON
 | RYBREVANT in Combination with Carboplatin and Pemetrexed [The denominator used to calculate the rate varied from 113 to 150 based on the number of patients with a baseline value and at least one post-treatment value.] |  | Carboplatin in Combination with Pemetrexed [The denominator used to calculate the rate varied from 119 to 154 based on the number of patients with a baseline value and at least one post-treatment value.]
Laboratory Abnormality [Adverse reactions were graded using CTCAE version 5.0] | All Grades (%) | Grade 3 or 4 (%) | All Grades (%) | Grade 3 or 4 (%)
Hematology
Decreased white blood cells | 89 | 17 | 76 | 10
Decreased hemoglobin | 79 | 11 | 85 | 13
Decreased neutrophils | 76 | 36 | 61 | 23
Decreased platelets | 70 | 10 | 54 | 12
Decreased lymphocytes | 61 | 11 | 49 | 13
Chemistry
Decreased albumin | 87 | 7 | 34 | 1
Increased aspartate aminotransferase | 60 | 1 | 61 | 1
Increased alanine aminotransferase | 57 | 4 | 54 | 1
Decreased sodium | 55 | 7 | 39 | 4
Increased alkaline phosphatase | 51 | 1 | 28 | 0
Decreased potassium | 44 | 11 | 17 | 1
Decreased magnesium | 39 | 2 | 30 | 1
Increased gamma-glutamyl transferase | 38 | 4 | 43 | 4
Decreased calcium (corrected) | 27 | 1 | 18 | 1

Previously Treated NSCLC Exon 20 Insertion Mutations

The safety data described below reflect exposure to RYBREVANT at the recommended dosage in 129 patients with locally advanced or metastatic NSCLC with EGFR exon 20 insertion mutations in the CHRYSALIS trial [see Clinical Studies (14.4)], whose disease had progressed on or after platinum-based chemotherapy. Among patients who received RYBREVANT, 44% were exposed for 6 months or longer and 12% were exposed for greater than one year.

The median age was 62 years (range: 36 to 84 years); 61% were female; 55% were Asian, 35% were White, and 2.3% were Black; and 82% had baseline body weight < 80 kg.

Serious adverse reactions occurred in 30% of patients who received RYBREVANT. Serious adverse reactions in ≥ 2% of patients included pulmonary embolism, pneumonitis/ILD, dyspnea, musculoskeletal pain, pneumonia, and muscular weakness. Fatal adverse reactions occurred in 2 patients (1.5%) due to pneumonia and 1 patient (0.8%) due to sudden death.

Permanent discontinuation of RYBREVANT due to an adverse reaction occurred in 11% of patients. Adverse reactions resulting in permanent discontinuation of RYBREVANT in ≥ 1% of patients were pneumonia, IRR, pneumonitis/ILD, dyspnea, pleural effusion, and rash.

Dose interruptions of RYBREVANT due to an adverse reaction occurred in 78% of patients. Infusion-related reactions (IRR) requiring infusion interruptions occurred in 59% of patients. Adverse reactions requiring dose interruption in ≥ 5% of patients included dyspnea, nausea, rash, vomiting, fatigue, and diarrhea.

Dose reductions of RYBREVANT due to an adverse reaction occurred in 15% of patients. Adverse reactions requiring dose reductions in ≥ 2% of patients included rash and paronychia.

The most common adverse reactions (≥ 20%) were rash, IRR, paronychia, musculoskeletal pain, dyspnea, nausea, fatigue, edema, stomatitis, cough, constipation, and vomiting. The most common Grade 3 to 4 laboratory abnormalities (≥ 2%) were decreased lymphocytes, decreased albumin, decreased phosphate, decreased potassium, increased glucose, increased alkaline phosphatase, increased gamma-glutamyl transferase, and decreased sodium.

Table 16 summarizes the adverse reactions in CHRYSALIS.

Table 16: Adverse Reactions (≥ 10%) in Patients with NSCLC with Exon 20 Insertion Mutations Whose Disease Has Progressed on or after Platinum-based Chemotherapy and Received RYBREVANT in CHRYSALIS
Adverse Reactions | RYBREVANT [Adverse reactions were graded using CTCAE version 4.03] (N=129)
Adverse Reactions | All Grades (%) | Grades 3 or 4 (%)
Skin and subcutaneous tissue disorders
Rash [Grouped term] | 84 | 3.9
Pruritus | 18 | 0
Dry skin | 14 | 0
General disorders and administration site conditions
Infusion-related reaction | 64 | 3.1
Fatigue | 33 | 2.3
Edema | 27 | 0.8
Pyrexia | 13 | 0
Infections and infestations
Paronychia | 50 | 3.1
Pneumonia | 10 | 0.8
Musculoskeletal and connective tissue disorders
Musculoskeletal pain | 47 | 0
Respiratory, thoracic, and mediastinal disorders
Dyspnea | 37 | 2.3
Cough | 25 | 0
Gastrointestinal disorders
Nausea | 36 | 0
Stomatitis | 26 | 0.8
Constipation | 23 | 0
Vomiting | 22 | 0
Diarrhea | 16 | 3.1
Abdominal Pain | 11 | 0.8
Vascular disorders
Hemorrhage | 19 | 0
Metabolism and nutrition disorders
Decreased appetite | 15 | 0
Nervous system disorders
Peripheral neuropathy | 13 | 0
Dizziness | 12 | 0.8
Headache | 10 | 0.8

Clinically relevant adverse reactions in < 10% of patients who received RYBREVANT included ocular toxicity, ILD/pneumonitis, and toxic epidermal necrolysis (TEN).

Table 17 summarizes the laboratory abnormalities in CHRYSALIS.

Table 17: Select Laboratory Abnormalities (≥ 20%) That Worsened from Baseline in Patients With Metastatic NSCLC with EGFR Exon 20 Insertion Mutations Whose Disease Has Progressed on or After Platinum-based Chemotherapy and Who Received RYBREVANT in CHRYSALIS
Laboratory Abnormality | RYBREVANT [The denominator used to calculate the rate was 126 based on the number of patients with a baseline value and at least one post-treatment value.] (N=129)
Laboratory Abnormality | All Grades (%) | Grades 3 or 4 (%)
Chemistry
Decreased albumin | 79 | 8
Increased glucose | 56 | 4
Increased alkaline phosphatase | 53 | 4.8
Increased creatinine | 46 | 0
Increased alanine aminotransferase | 38 | 1.6
Decreased phosphate | 33 | 8
Increased aspartate aminotransferase | 33 | 0
Decreased magnesium | 27 | 0
Increased gamma-glutamyl transferase | 27 | 4
Decreased sodium | 27 | 4
Decreased potassium | 26 | 6
Hematology
Decreased lymphocytes | 36 | 8

6.2 Postmarketing Experience

The following adverse reactions associated with the use of RYBREVANT were identified in clinical studies or postmarketing reports. Because some of these reactions were reported voluntarily from a population of uncertain size, it is not always possible to reliably estimate their frequency or establish a causal relationship to drug exposure.

Immune system disorders: Infusion-related reactions, including anaphylaxis/anaphylactic reactions

8 USE IN SPECIFIC POPULATIONS

8.1 Pregnancy

Risk Summary

Based on the mechanism of action and findings in animal models, RYBREVANT can cause fetal harm when administered to a pregnant woman. There are no available data on the use of RYBREVANT in pregnant women or animal data to assess the risk of RYBREVANT in pregnancy. Disruption or depletion of EGFR in animal models resulted in impairment of embryo-fetal development including effects on placental, lung, cardiac, skin, and neural development. The absence of EGFR or MET signaling has resulted in embryo lethality, malformations, and post-natal death in animals (see Data). Advise pregnant women of the potential risk to a fetus.

In the U.S. general population, the estimated background risk of major birth defects and miscarriage in clinically recognized pregnancies is 2% to 4% and 15% to 20%, respectively.

Data

Animal Data

No animal studies have been conducted to evaluate the effects of amivantamab-vmjw on reproduction and fetal development; however, based on its mechanism of action, RYBREVANT can cause fetal harm or developmental anomalies. In mice, EGFR is critically important in reproductive and developmental processes including blastocyst implantation, placental development, and embryo-fetal/postnatal survival and development. Reduction or elimination of embryo-fetal or maternal EGFR signaling can prevent implantation, can cause embryo-fetal loss during various stages of gestation (through effects on placental development) and can cause developmental anomalies and early death in surviving fetuses. Adverse developmental outcomes were observed in multiple organs in embryos/neonates of mice with disrupted EGFR signaling. Similarly, knock out of MET or its ligand HGF was embryonic lethal due to severe defects in placental development, and fetuses displayed defects in muscle development in multiple organs. Human IgG1 is known to cross the placenta; therefore, amivantamab-vmjw has the potential to be transmitted from the mother to the developing fetus.

8.2 Lactation

Risk Summary

There are no data on the presence of amivantamab-vmjw in human milk, the effects on the breastfed child or on milk production. Because of the potential for serious adverse reactions from RYBREVANT in breast-fed children, advise women not to breastfeed during treatment with RYBREVANT and for 3 months after the last dose.

8.3 Females and Males of Reproductive Potential

RYBREVANT can cause fetal harm when administered to a pregnant woman [see Use in Specific Populations (8.1)].

Pregnancy Testing

Verify pregnancy status of females of reproductive potential prior to initiating RYBREVANT.

Contraception

Females

Advise females of reproductive potential to use effective contraception during treatment and for 3 months after the last dose of RYBREVANT.

8.4 Pediatric Use

The safety and efficacy of RYBREVANT have not been established in pediatric patients.

8.5 Geriatric Use

- Of the 421 patients with locally advanced or metastatic NSCLC treated with RYBREVANT in combination with lazertinib in the MARIPOSA study, 45% were ≥ 65 years of age and 12% were ≥ 75 years of age.
- Of the 130 patients with locally advanced or metastatic NSCLC treated with RYBREVANT in combination with carboplatin and pemetrexed in the MARIPOSA-2 study, 40% were ≥ 65 years of age and 10% were ≥ 75 years of age.
- Of the 151 patients with locally advanced or metastatic NSCLC treated with RYBREVANT in combination with carboplatin and pemetrexed in the PAPILLON study, 37% were ≥ 65 years of age and 8% were ≥ 75 years of age.
- Of the 302 patients with locally advanced or metastatic NSCLC treated with RYBREVANT as a single agent in the CHRYSALIS study, 39% were ≥ 65 years of age and 11% were ≥ 75 years of age.

No clinically important differences in safety or efficacy were observed between patients who were ≥ 65 years of age and younger patients.

11 DESCRIPTION

Amivantamab-vmjw is a low-fucose human immunoglobulin G1-based bispecific antibody directed against the EGF and MET receptors, produced by mammalian cell line (Chinese Hamster Ovary [CHO]) using recombinant DNA technology that has a molecular weight of approximately 148 kDa. RYBREVANT® (amivantamab-vmjw) injection for intravenous infusion is a sterile, preservative-free, colorless to pale yellow solution in single-dose vials. The pH is 5.7.

Each RYBREVANT vial contains 350 mg (50 mg/mL) amivantamab-vmjw, EDTA disodium salt dihydrate (0.14 mg), L-histidine (2.3 mg), L-histidine hydrochloride monohydrate (8.6 mg), L-methionine (7 mg), polysorbate 80 (4.2 mg), sucrose (595 mg), and water for injection, USP.

12 CLINICAL PHARMACOLOGY

12.1 Mechanism of Action

Amivantamab-vmjw is a bispecific antibody that binds to the extracellular domains of EGFR and MET.

In in vitro and in vivo studies amivantamab-vmjw was able to disrupt EGFR and MET signaling functions in mutation models of exon 19 deletions, exon 21 L858R substitutions, and exon 20 insertions through blocking ligand binding or degradation of EGFR and MET. The presence of EGFR and MET on the surface of tumor cells also allows for targeting of these cells for destruction by immune effector cells, such as natural killer cells and macrophages, through antibody-dependent cellular cytotoxicity (ADCC) and trogocytosis mechanisms, respectively. Treatment with amivantamab in combination with lazertinib increased in vivo anti-tumor activity compared to either agent alone in a mouse xenograft model of human NSCLC with an EGFR L858R mutation.

12.2 Pharmacodynamics

The exposure-response relationship and time-course of pharmacodynamic response of amivantamab-vmjw have not been fully characterized in patients with NSCLC with EGFR mutations.

12.3 Pharmacokinetics

Amivantamab-vmjw exposures increased proportionally over a dosage range from 350 to 1,750 mg (0.33 to 1.7 times the lowest approved recommended dosage) when RYBREVANT was administered as a single agent. Steady-state concentrations of RYBREVANT were reached by week 13 for both the 3-week and 2-week dosing regimen and the systemic accumulation was 1.9-fold.

Distribution

The amivantamab-vmjw mean (%CV) volume of distribution is 5 (24%) L.

Elimination

The mean (% CV) linear clearance (CL) is 0.26 L/day (30%) and mean terminal half-life is 14 days (33%).

Specific Populations

No clinically meaningful differences in the pharmacokinetics of amivantamab-vmjw were observed based on age (range: 21–88 years), body weight (31 to 140 kg), sex, race (White, Asian or Black or African American) and ethnicity (Hispanic/Latino or not Hispanic/Latino), mild or moderate renal impairment (eGFR 30 to 89 mL/min) or mild hepatic impairment [(total bilirubin ≤ ULN and AST > ULN) or (ULN < total bilirubin ≤ 1.5 times ULN)]. The effect of severe renal impairment (eGFR 15 to 29 mL/min), end-stage renal disease (eGFR < 15 mL/min) or moderate to severe hepatic impairment (total bilirubin > 1.5 times ULN and any AST) on amivantamab-vmjw pharmacokinetics has not been studied.

Body Weight

Increases in body weight increased the volume of distribution and clearance of amivantamab-vmjw. Amivantamab-vmjw exposures are 30 to 40% lower in patients who weighed ≥ 80 kg compared to patients with body weight < 80 kg at the same dose. Exposures of amivantamab-vmjw were comparable between patients who weighed < 80 kg and received 1,050 mg dose and patients who weighed ≥ 80 kg and received 1,400 mg dose.

12.6 Immunogenicity

The observed incidence of anti-drug antibodies is highly dependent on the sensitivity and specificity of the assay. Differences in assay methods preclude meaningful comparisons of the incidence of anti-drug antibodies (ADA) in the studies described below with the incidence of anti-drug antibodies in other studies, including those of amivantamab-vmjw or amivantamab products.

During treatment in studies CHRYSALIS, CHRYSALIS-2, PAPILLON, MARIPOSA, and MARIPOSA-2 (up to 39 months), 4 of the 1,862 (0.2%) patients who received RYBREVANT as a single agent or in combination developed a treatment-emergent anti-amivantamab-vmjw antibodies. Given the low occurrence of anti-drug antibodies, the effect of these antibodies on the pharmacokinetics, safety or efficacy of RYBREVANT is unknown.

13 NONCLINICAL TOXICOLOGY

13.1 Carcinogenesis, Mutagenesis, Impairment of Fertility

No studies have been performed to assess the potential of amivantamab-vmjw for carcinogenicity or genotoxicity. Fertility studies have not been performed to evaluate the potential effects of amivantamab-vmjw. In 6-week and 3-month repeat-dose toxicology studies in monkeys, there were no notable effects in the male and female reproductive organs.

14 CLINICAL STUDIES

14.1 First Line Treatment of NSCLC with Exon 19 deletion or Exon 21 L858R Substitution Mutation - MARIPOSA

The efficacy of RYBREVANT, in combination with lazertinib, was evaluated in MARIPOSA [NCT04487080], a randomized, active-controlled, multicenter trial. Eligible patients were required to have untreated locally advanced or metastatic NSCLC with either exon 19 deletions or exon 21 L858R substitution EGFR mutations identified by local testing, not amenable to curative therapy. Patients with asymptomatic or previously treated and stable intracranial metastases were eligible to enroll.

Patients were randomized (2:2:1) to receive RYBREVANT in combination with lazertinib (N=429), osimertinib monotherapy (N=429), or lazertinib monotherapy (an unapproved regimen for NSCLC) until disease progression or unacceptable toxicity. The evaluation of efficacy for the treatment of untreated metastatic NSCLC relied upon comparison between:

- RYBREVANT administered intravenously at 1,050 mg (for patients < 80 kg) or 1,400 mg (for patients ≥ 80 kg) once weekly for 4 weeks, then every 2 weeks thereafter starting at week 5 in combination with lazertinib administered at 240 mg orally once daily.
- Osimertinib administered at a dose of 80 mg orally once daily.

Randomization was stratified by EGFR mutation type (exon 19 deletion or exon 21 L858R substitution mutation), Asian race (yes or no), and history of brain metastasis (yes or no). Tumor assessments were performed every 8 weeks for 30 months, and then every 12 weeks until disease progression.

The major efficacy outcome measure was progression-free survival (PFS) as assessed by blinded independent central review (BICR). Additional efficacy outcome measures included overall survival (OS), overall response rate (ORR), and duration of response (DOR).

A total of 858 patients were randomized between the two study arms, 429 to the RYBREVANT in combination with lazertinib arm and 429 to the osimertinib arm. The median age was 63 (range: 25–88) years; 61% were female; 58% were Asian, 38% were White, 1.6% were American Indian or Alaska Native, 0.8% were Black or African American, 0.2% were Native Hawaiian or other Pacific Islander, 0.6% were unknown race or multiple races; and 12% were Hispanic or Latino. Eastern Cooperative Oncology Group (ECOG) performance status was 0 (34%) or 1 (66%); 69% never smoked; 41% had prior brain metastases; and 89% had Stage IV cancer at initial diagnosis. Sixty percent of patients had tumors harboring exon 19 deletions and the remaining 40% had exon 21 L858R substitution mutations.

Among the 858 patients with EGFR exon 19 deletion or L858R substitution mutations that were randomized between the RYBREVANT plus lazertinib arm versus the osimertinib arm, available tissue samples from 544 (63%) patients had evaluable results when tested retrospectively using the cobas EGFR Mutation Test v2. Of the 544 patients with evaluable results, 527 (97%) patients were positive for EGFR exon 19 deletion or L858R substitution mutations, while 17 (3%) patients were negative. Available plasma samples from patients were retrospectively tested using an FDA-approved test to confirm the biomarker status.

The trial demonstrated a statistically significant improvement in PFS by BICR assessment and OS for RYBREVANT in combination with lazertinib compared to osimertinib (see Table 18 and Figures 1 and 2).

Efficacy results for RYBREVANT in combination with lazertinib are provided in Table 18.

Table 18: Efficacy Results in MARIPOSA by BICR Assessment
 | RYBREVANT in combination with lazertinib (N=429) | Osimertinib (N=429)
Progression-free survival (PFS)
Number of events (%) | 192 (45) | 252 (59)
Median, months (95% CI) | 23.7 (19.1, 27.7) | 16.6 (14.8, 18.5)
HR [Stratified by mutation type (Exon 19del or Exon 21 L858R), prior brain metastases (yes or no), and Asian race (yes or no).] , [Stratified Cox proportional hazards regression.] (95% CI); p-value , [Stratified log-rank test.] | 0.70 (0.58, 0.85); p=0.0002
Overall survival (OS)
Number of events (%) | 173 (40) | 217 (51)
Median, months (95% CI) | NR (42.9, NE) | 36.7 (33.4, 41.0)
HR ,(95% CI); p-value , | 0.75 (0.61, 0.92); p=0.0048
Overall response rate (ORR) [Confirmed responses based on the ITT population.]
ORR, % (95% CI) | 78 (74, 82) | 73 (69, 78)
Complete response, % | 5.4 | 3.5
Partial response, % | 73 | 70
Duration of response (DOR) [In confirmed responders.]
Median (95% CI), months | 25.8 (20.1, NE) | 16.7 (14.8, 18.5)
Patients with DOR ≥ 6 months [Based on observed rates.] , % | 86 | 85
Patients with DOR ≥ 12 months , % | 68 | 57
CI = confidence interval; NR = not reached; NE = not estimable

Figure 1: Kaplan-Meier Curves of PFS by BICR Assessment in Patients with Previously Untreated NSCLC

Figure 2: Kaplan-Meier Curves of OS in Patients with Previously Untreated NSCLC

Out of all randomized patients (n=858), 367 (43%) had baseline intracranial lesions assessed by BICR using modified RECIST. Results of pre-specified analyses of intracranial ORR and DOR by BICR in the subset of patients with intracranial lesions at baseline for the RYBREVANT in combination with lazertinib arm and the osimertinib arm are summarized in Table 19.

Table 19: Exploratory Analysis of Intracranial ORR and DOR by BICR Assessment in Subjects with Intracranial Lesions at Baseline
 | RYBREVANT in combination with lazertinib (N=180) | Osimertinib (N=187)
Intracranial tumor response assessment
Intracranial ORR [Confirmed responses] , % (95% CI) | 68 (60, 75) | 69 (62, 76)
Complete response % | 55 | 52
Intracranial DOR [In confirmed responders]
Number of responders | 122 | 129
Patients with DOR ≥ 12 months [Based on observed rates] , % | 66 | 59
Patients with DOR ≥ 18 months , % | 35 | 23
CI = confidence interval

14.2 Previously Treated NSCLC Patients with EGFR Exon 19 Deletions or Exon 21 L858R Substitution Mutations - MARIPOSA-2

The efficacy of RYBREVANT in combination with carboplatin and pemetrexed was evaluated in MARIPOSA-2 (NCT04988295), a randomized, open-label, multicenter trial. Eligible patients were required to have locally advanced or metastatic NSCLC with EGFR exon 19 deletions or exon 21 L858R substitution mutations and progressive disease on or after receiving osimertinib. Patients with asymptomatic or previously treated and stable intracranial metastases were eligible to enroll. Patients were randomized (1:2:2) to receive RYBREVANT in combination with carboplatin and pemetrexed (RYBREVANT-CP, N=131), carboplatin and pemetrexed (CP, N=263), or RYBREVANT as part of another combination regimen. The evaluation of efficacy for metastatic NSCLC relied upon comparison between:

- RYBREVANT in combination with carboplatin and pemetrexed. RYBREVANT was administered intravenously at 1,400 mg (for patients < 80 kg) or 1,750 mg (for patients ≥ 80 kg) once weekly through 4 weeks, then every 3 weeks with a dose of 1,750 mg (for patients < 80 kg) or 2,100 mg (for patients ≥ 80 kg) starting at Week 7 until disease progression or unacceptable toxicity.
- Platinum-based chemotherapy with carboplatin and pemetrexed.

For both arms, carboplatin was administered intravenously at area under the concentration-time curve 5 mg/mL per minute (AUC 5) once every 3 weeks, for up to 12 weeks and pemetrexed was administered intravenously at 500 mg/m^2 once every 3 weeks until disease progression or unacceptable toxicity.

Randomization was stratified by osimertinib line of therapy (first-line or second-line), prior brain metastases (yes or no), and Asian race (yes or no). Tumor assessments were performed every 6 weeks for the first 12 months and every 12 weeks thereafter.

The major efficacy outcome measure was progression-free survival (PFS) as assessed by blinded independent central review (BICR). Overall survival (OS) and overall response rate (ORR) as assessed by BICR were key secondary outcome measures.

A total of 394 patients were randomized between the two arms, 131 to the RYBREVANT-CP arm and 263 to the CP arm. The median age was 62 (range: 31 to 85) years, with 38% of patients ≥ 65 years of age; 60% were female; and 48% were Asian and 46% were White, 1% were American Indian or Alaska Native, 1% were Black or African American, 0.5% were multiple races and 2.8% were race not reported or race unknown; 8% were Hispanic or Latino. Baseline Eastern Cooperative Oncology Group (ECOG) performance status was 0 (40%) or 1 (60%); 65% never smoked; 45% had history of brain metastasis, and 99.7% had Stage IV cancer at study enrollment.

The trial demonstrated a statistically significant improvement in PFS by BICR for RYBREVANT in combination with carboplatin and pemetrexed compared to carboplatin and pemetrexed.

Efficacy results are summarized in Table 20.

Table 20: Efficacy results in MARIPOSA-2
 | RYBREVANT + carboplatin+ pemetrexed (N=131) | carboplatin+ pemetrexed (N=263)
Progression-free survival (PFS) [Blinded Independent Central Review by RECIST v1.1]
Number of events | 74 (56%) | 171 (65%)
Median, months (95% CI) | 6.3 (5.6, 8.4) | 4.2 (4.0, 4.4)
HR (95% CI) [Stratified by osimertinib line of therapy (first-line or second-line), prior brain metastases (yes or no), and Asian race (yes or no).] , [Stratified Cox proportional hazards regression.] ; p-value , [Stratified log-rank test.] | 0.48 (0.36, 0.64); p<0.0001
Overall response rate, [Confirmed responses.]
ORR, % (95% CI) | 53% (44, 62) | 29% (23, 35)
p-value , [Stratified logistic regression analysis.] | p<0.0001
Complete response | 0.8% | 0%
Partial response | 52% | 29%
Duration of response, (DOR)
Median (95% CI), months | 6.9 (5.5, NE) | 5.6 (4.2, 9.6)
CI = confidence interval; NE = not estimable

Figure 3: Kaplan-Meier curve of PFS in Previously Treated NSCLC Patients by BICR assessment- MARIPOSA-2

At the prespecified second interim analysis of OS, with 85% of the deaths needed for the final analysis, there was no statistically significant difference in OS. The median OS was 17.7 months (95% CI: 16.0, 22.4) in the ACP arm and 15.3 months (95% CI: 13.7, 16.8) in the CP arm, with a hazard ratio of 0.73 (95% CI: 0.54, 0.99).

Patients with asymptomatic or previously treated and stable intracranial metastases were eligible to be randomized in MARIPOSA-2. Baseline disease assessment, including brain magnetic resonance imaging (MRI) was performed at treatment initiation. All patients underwent serial brain MRI during the trial.

Pre-specified secondary analyses of intracranial ORR by BICR in the subset of 91 (23%) patients with baseline intracranial disease were performed. Data were only available for intracranial complete responses and not available for intracranial partial responses. Intracranial ORR was 20% (95% CI: 8, 39) in the 30 patients with baseline intracranial disease in the ACP arm and 7% (95% CI: 1.8, 16) in the 61 patients with baseline intracranial disease in the CP arm.

14.3 First Line Treatment of NSCLC with Exon 20 Insertion Mutations - PAPILLON

The efficacy of RYBREVANT was evaluated in PAPILLON (NCT04538664), in a randomized, open-label, multicenter study. Eligible patients were required to have previously untreated locally advanced or metastatic NSCLC with EGFR Exon 20 insertion mutations measurable disease per RECIST v1.1, Eastern Cooperative Oncology Group (ECOG) performance status (PS) ≤ 1, and adequate organ and bone marrow function. Patients with brain metastases at screening were eligible for participation once they were definitively treated, clinically stable, asymptomatic, and off corticosteroid treatment for at least 2 weeks prior to randomization. Patients with a medical history of interstitial lung disease or active ILD were excluded from the clinical study.

A total of 308 patients were randomized 1:1 to receive RYBREVANT in combination with carboplatin and pemetrexed (n=153) or carboplatin and pemetrexed (n=155). Patients received RYBREVANT intravenously at 1,400 mg (for patients < 80 kg) or 1,750 mg (for patients ≥ 80 kg) once weekly through 4 weeks, then every 3 weeks with a dose of 1,750 mg (for patients < 80 kg) or 2,100 mg (for patients ≥ 80 kg) starting at Week 7 until disease progression or unacceptable toxicity. Carboplatin was administered intravenously at area under the concentration-time curve 5 mg/mL per minute (AUC 5) once every 3 weeks, for up to 12 weeks. Pemetrexed was administered intravenously at 500 mg/m^2 on once every 3 weeks until disease progression or unacceptable toxicity. Patients were stratified by Eastern Cooperative Oncology Group (ECOG) performance status (0 or 1) and prior brain metastases (yes or no).

The primary efficacy outcome measure was progression-free survival (PFS) as assessed by blinded independent central review (BICR). Additional efficacy outcome measures included overall response rate (ORR), duration of response (DOR) and overall survival (OS). Cross-over to single agent RYBREVANT was permitted for patients who had confirmed disease progression on carboplatin and pemetrexed.

The median age was 62 (range: 27 to 92) years, with 40% of the patients ≥ 65 years of age; 58% were female; 61% were Asian and 36% were White, 0.7% were Black or African American and race was not reported in 2.3% of patients; 93% were not Hispanic or Latino. Baseline ECOG performance status was 0 (35%) or 1 (65%); 58% were never smokers; 23% had history of brain metastasis and 84% had Stage IV cancer at initial diagnosis.

PAPILLON demonstrated a statistically significant improvement in progression free survival for patients randomized to RYBREVANT in combination with carboplatin and pemetrexed compared with carboplatin and pemetrexed.

Efficacy results are summarized in Table 21 and Figure 4.

Table 21: Efficacy Results in PAPILLON
 | RYBREVANT+ carboplatin+ pemetrexed (N=153) | carboplatin+ pemetrexed (N=155)
Progression-free survival (PFS)
Number of events (%) | 84 (55) | 132 (85)
Median, months (95% CI) | 11.4 (9.8, 13.7) | 6.7 (5.6, 7.3)
HR (95% CI) | 0.40 (0.30, 0.53)
p-value | p<0.0001
Overall response rate (ORR) [Confirmed responses.]
ORR, % (95% CI) | 67 (59, 75) | 36 (29, 44)
Complete response, % | 4 | 1
Partial response, % | 63 | 36
Duration of response (DOR) [In confirmed responders.]
Median (95% CI), months | 10.1 (8.5, 13.9) | 5.6 (4.4, 6.9)
CI = confidence interval

Figure 4: Kaplan-Meier Curve of PFS in Previously Untreated NSCLC Patients by BICR Assessment – PAPILLON Study

While OS results were immature at the current analysis, with 44% of pre-specified deaths for the final analysis reported, no trend towards a detriment was observed. Seventy-five (48%) of the treated patients crossed over from the carboplatin and pemetrexed arm after confirmation of disease progression to receive RYBREVANT as a single agent.

14.4 Previously Treated NSCLC with Exon 20 Insertion Mutations - CHRYSALIS

The efficacy of RYBREVANT was evaluated in patients with locally advanced or metastatic NSCLC with EGFR exon 20 insertion mutations in a multicenter, open-label, multi-cohort clinical trial (CHRYSALIS, NCT02609776). The study included patients with locally advanced or metastatic NSCLC with EGFR exon 20 insertion mutations whose disease had progressed on or after platinum-based chemotherapy. Patients with untreated brain metastases and patients with a history of ILD requiring treatment with prolonged steroids or other immunosuppressive agents within the last 2 years were not eligible for the study.

In the efficacy population, EGFR exon 20 insertion mutation status was determined by prospective local testing using tissue (94%) and/or plasma (6%) samples. Of the 81 patients with EGFR exon 20 insertion mutations identified by local testing, plasma samples from 78/81 (96%) patients were tested retrospectively using Guardant360®CDx, identifying 62/78 (79%) samples with an EGFR exon 20 insertion mutation; 16/78 (21%) samples did not have an EGFR exon 20 insertion mutation identified.

Patients received RYBREVANT at 1,050 mg (for patient baseline body weight < 80 kg) or 1,400 mg (for patient baseline body weight ≥ 80 kg) once weekly for 4 weeks, then every 2 weeks thereafter until disease progression or unacceptable toxicity. The major efficacy outcome measure was overall response rate (ORR) according to Response Evaluation Criteria in Solid Tumors (RECIST v1.1) as evaluated by Blinded Independent Central Review (BICR). An additional efficacy outcome measure was duration of response (DOR) by BICR.

The efficacy population included 81 patients with NSCLC with EGFR exon 20 insertion mutation with measurable disease who were previously treated with platinum-based chemotherapy. The median age was 62 (range: 42 to 84) years, 59% were female; 49% were Asian, 37% were White, 2.5% were Black; 74% had baseline body weight < 80 kg; 95% had adenocarcinoma; and 46% had received prior immunotherapy. The median number of prior therapies was 2 (range: 1 to 7). At baseline, 67% had Eastern Cooperative Oncology Group (ECOG) performance status of 1; 53% never smoked; all patients had metastatic disease; and 22% had previously treated brain metastases.

Efficacy results are summarized in Table 22.

Table 22: Efficacy Results for CHRYSALIS
 | Prior Platinum-based Chemotherapy Treated (N=81)
Overall response rate(95% CI) | 40% (29%, 51%)
Complete response (CR) | 3.7%
Partial response (PR) | 36%
Duration of response (DOR)
Median, months (95% CI), months | 11.1 (6.9, NE)
Patients with DOR ≥ 6 months | 63%
Based on Kaplan-Meier estimates.
NE=Not Estimable; CI=confidence interval.

16 HOW SUPPLIED/STORAGE AND HANDLING

How Supplied

RYBREVANT® (amivantamab-vmjw) injection is a sterile, preservative-free, colorless to pale yellow solution for intravenous infusion. Each single-dose vial contains 350 mg/7 mL (50 mg/mL) RYBREVANT. Each vial is individually packed in a single carton. (NDC 57894-501-01).

Storage and Handling

Store in a refrigerator at 2°C to 8°C (36°F to 46°F) in original carton to protect from light. Do not freeze.

17 PATIENT COUNSELING INFORMATION

Advise the patient to read the FDA-approved patient labeling (Patient Information).

Infusion-Related Reactions

Advise patients that RYBREVANT can cause infusion-related reactions (IRR), including anaphylaxis. Instruct patients to take glucocorticoids 48 hours prior to the first RYBREVANT infusion to reduce the risk of IRR [see Dosage and Administration (2.5)]. The majority of infusion-related reactions occurred with the first infusion. Advise patients to alert their healthcare provider immediately for any signs or symptoms of infusion-related reactions [see Warnings and Precautions (5.1)] .

Interstitial Lung Disease/Pneumonitis

Advise patients of the risks of interstitial lung disease (ILD)/pneumonitis. Advise patients to immediately contact their healthcare provider for new or worsening respiratory symptoms [see Warnings and Precautions (5.2)] .

Venous Thromboembolic Events with Concomitant Use with Lazertinib

When RYBREVANT is used in combination with lazertinib, advise patients of the risks of serious and life threatening venous thromboembolic (VTE) events, including deep venous thrombosis and pulmonary embolism. Advise patients that prophylactic anticoagulants are recommended to be used for the first four months of treatment. Advise patients to immediately contact their healthcare provider for signs and symptoms of venous thromboembolism [see Warnings and Precautions (5.3)] .

Dermatologic Adverse Reactions

Advise patients of the risk of dermatologic adverse reactions. Advise patients that prophylactic oral antibiotics are recommended starting on Day 1 for the first 12 weeks of treatment and, after completion of oral antibiotic treatment, topical antibiotic lotion to the scalp for the next 9 months of treatment. Advise patients to use a non-comedogenic skin moisturizer (ceramide-based or other formulations that provide long-lasting skin hydration and exclude drying components) on the face and whole body (except scalp) and 4% chlorhexidine solution to wash hands and feet, while on treatment. Advise patients to limit direct sun exposure during and for 2 months after treatment, to wear protective clothing, and to use broad-spectrum UVA/UVB sunscreen to reduce the risk and severity of dermatologic adverse reactions [see Warnings and Precautions (5.4)] .

Ocular Toxicity

Advise patients of the risk of ocular toxicity. Advise patients to contact their ophthalmologist if they develop eye symptoms and advise discontinuation of contact lenses until symptoms are evaluated [see Warnings and Precautions (5.5)] .

Paronychia/Nail Toxicity

Advise patients of the risk of paronychia. Advise patients to contact their healthcare provider for signs or symptoms of paronychia [see Adverse Reactions (6.1)].

Embryo-Fetal Toxicity

Advise females of reproductive potential of the potential risk to a fetus, to use effective contraception during treatment with RYBREVANT and for 3 months after the last dose, and to inform their healthcare provider of a known or suspected pregnancy [see Warnings and Precautions (5.6), Use in Specific Populations (8.1, 8.3)].

Lactation

Advise women not to breastfeed during treatment with RYBREVANT and for 3 months after the last dose [see Use in Specific Populations (8.2)] .

Product of Ireland

Manufactured by:
Janssen Biotech, Inc.
Horsham, PA 19044, USA
U.S. License Number 1864

For patent information: www.janssenpatents.com
© Johnson & Johnson and its affiliates 2021-2025

PATIENT INFORMATION
RYBREVANT® (RYE–breh–vant)
(amivantamab-vmjw)
injection, for intravenous use

What is RYBREVANT?
RYBREVANT is a prescription medicine used to treat adults with non-small cell lung cancer (NSCLC) that has spread to other parts of the body (metastatic) or cannot be removed by surgery, and has certain abnormal epidermal growth factor receptor (EGFR) gene(s):

- in combination with lazertinib as a first-line treatment for non-small cell lung cancer (NSCLC)
- in combination with carboplatin and pemetrexed as a second-line treatment for NSCLC in patients whose disease has worsened on or after treatment with an EGFR tyrosine kinase inhibitor (TKI)
- in combination with carboplatin and pemetrexed as a first-line treatment for NSCLC
- alone for the treatment of NSCLC whose disease has worsened on or after platinum-based chemotherapy.

Your healthcare provider will perform a test to make sure that RYBREVANT is right for you.
It is not known if RYBREVANT is safe and effective in children.

Before you receive RYBREVANT, tell your healthcare provider about all of your medical conditions, including if you:

- have a history of lung or breathing problems
- are pregnant or plan to become pregnant. RYBREVANT can harm your unborn baby.
  Females who are able to become pregnant:
  - Your healthcare provider should do a pregnancy test before you start treatment with RYBREVANT.
  - You should use effective birth control (contraception) during treatment and for 3 months after your last dose of RYBREVANT.
  - Tell your healthcare provider right away if you become pregnant or think you might be pregnant during treatment with RYBREVANT.
- are breastfeeding or plan to breastfeed. It is not known if RYBREVANT passes into your breast milk. Do not breastfeed during treatment and for 3 months after your last dose of RYBREVANT.

Tell your healthcare provider about all the medicines you take,including prescription and over-the-counter medicines, vitamins, and herbal supplements.

How will I receive RYBREVANT?

- RYBREVANT will be given to you by your healthcare provider by intravenous infusion into your vein.
- Your healthcare provider will decide the time between doses as well as how many treatments you will receive.
- Your healthcare provider will give you medicines before each dose of RYBREVANT to help reduce the risk of infusion-related reactions.
- Your healthcare provider may give you medicines in addition to RYBREVANT to reduce the risk and severity of skin and nail reactions.
- RYBREVANT may be given in combination with the medicines carboplatin and pemetrexed. If you have any questions about these medicines, ask your healthcare provider.
- If your treatment with RYBREVANT is given in combination with the medicine lazertinib, you should take your dose of lazertinib by mouth anytime before your infusion with RYBREVANT.
- If you miss any appointments, call your healthcare provider as soon as possible to reschedule your appointment.

What should I avoid while receiving RYBREVANT?

RYBREVANT can cause skin reactions. You should limit your time in the sun during and for 2 months after your treatment with RYBREVANT. Wear protective clothing and use broad-spectrum UVA/UVB sunscreen during treatment with RYBREVANT.

What are the possible side effects of RYBREVANT?
RYBREVANT may cause serious side effects, including:

- infusion-related reactions. Infusion-related reactions are common but can be severe or serious and can include life-threatening (anaphylaxis) allergic reaction. Tell your healthcare provider right away if you get any of the following symptoms during your infusion of RYBREVANT:

- shortness of breath, difficulty breathing, or wheezing
- chest discomfort
- swelling of your eyes, lips, or tongue
- fever
- chills
- numbness of the tongue, lips, cheeks, or gums

- flushing
- skin rash, hives, or itching
- nausea or vomiting
- stomach cramps
- lightheadedness, dizziness, or fainting
- headache

- lung problems. RYBREVANT may cause lung problems that may lead to death. Symptoms may be similar to those symptoms from lung cancer. Tell your healthcare provider right away if you get any new or worsening lung symptoms, including shortness of breath, cough, or fever.
- blood clot problems. Blood clots are a serious, but common side effect of RYBREVANT, when given together with another drug called lazertinib, may cause blood clots in the veins of your legs (deep vein thrombosis) or lungs (pulmonary embolism) that may lead to death. Your healthcare provider will start you on medicine to reduce the risk of blood clots for the first 4 months of treatment. Tell your healthcare provider right away if you have any signs and symptoms of blood clots, including swelling, pain or tenderness in the leg, sudden unexplained chest pain, or shortness of breath.
- skin problems. RYBREVANT can cause severe rash; including blisters, peeling, skin pain and sores, redness, raised acne-like bumps, itching, and dry skin. Tell your healthcare provider right away if you get any skin reactions. Your healthcare provider may start you on an antibiotic for the first 3 months of treatment followed by an antibiotic lotion for your scalp for the next 9 months. During treatment with RYBREVANT, you should apply a non-comedogenic (does not clog pores) skin moisturizer (ceramide-based or other types of moisturizers that provide long-lasting skin hydration and does not include drying ingredients) on your face and whole body (except scalp) and wash your hands and feet every day with 4% chlorhexidine solution. Your healthcare provider may treat you with a medicine(s) or send you to see a skin specialist (dermatologist) if you get skin reactions during treatment with RYBREVANT. See "What should I avoid while receiving RYBREVANT?"
- eye problems. RYBREVANT may cause eye problems. Tell your healthcare provider right away if you get symptoms of eye problems which may include:

- eye pain
- inflammation of eye lids
- dry eyes
- eye redness
- blurred vision

- changes in vision
- itchy eyes
- excessive tearing
- sensitivity to light

Your healthcare provider may send you to see an eye specialist (ophthalmologist) if you get new or worsening eye problems during treatment with RYBREVANT. You should not use contact lenses until your eye symptoms are checked by a healthcare provider.

The most common side effects of RYBREVANT when given in combination with lazertinib include:

- rash
- infected skin around the nail
- muscle and joint pain
- sores in the mouth
- swelling of hands, ankles, feet, face, or all of your body
- unusual feeling in the skin (such as tingling or a crawling feeling)
- feeling very tired

- diarrhea
- constipation
- COVID-19
- dry skin
- bleeding
- decreased appetite
- itchy skin
- nausea
- changes in certain blood tests

The most common side effects of RYBREVANT when given in combination with carboplatin and pemetrexed include:

- rash
- infected skin around the nail
- feeling very tired
- nausea
- sores in the mouth
- constipation
- swelling of hands, ankles, feet, face, or all of your body

- decreased appetite
- muscle and joint pain
- vomiting
- COVID-19
- changes in certain blood tests

The most common side effects of RYBREVANT when given alone:

- rash
- infected skin around the nail
- muscle and joint pain
- shortness of breath
- nausea
- feeling very tired

- swelling of hands, ankles, feet, face, or all of your body
- sores in the mouth
- cough
- constipation
- vomiting
- changes in certain blood tests

Your healthcare provider may temporarily stop, decrease your dose, or completely stop your treatment with RYBREVANT if you have serious side effects.
These are not all of the possible side effects of RYBREVANT.
Call your doctor for medical advice about side effects. You may report side effects to FDA at 1-800-FDA-1088.

General information about safe and effective use of RYBREVANT
Medicines are sometimes prescribed for purposes other than those listed in a Patient Information leaflet. You can ask your healthcare provider or pharmacist for information about RYBREVANT that is written for health professionals.

What are the ingredients of RYBREVANT?
Active ingredient: amivantamab-vmjw
Inactive ingredients: EDTA disodium salt dihydrate, L-histidine, L-histidine hydrochloride monohydrate, L-methionine, polysorbate 80, sucrose, and water for injection.
Product of Ireland
Manufactured by: Janssen Biotech, Inc., Horsham, PA 19044, USA. U.S. License Number 1864
For patent information: www.janssenpatents.com
© Johnson & Johnson and its affiliates 2021-2025
For more information, call 1-800-526-7736 or go to www.RYBREVANT.com.

This Patient Information has been approved by the U.S. Food and Drug Administration.

Revised: 11/2025

PRINCIPAL DISPLAY PANEL - 7 mL Vial Carton

NDC 57894-501-01

Rybrevant®
(amivantamab-vmjw)
Injection

350 mg/7 mL
(50 mg/mL)

For Intravenous Infusion Only
Dilute Before Use

Rx only
7 mL Vial

janssen

Single-dose vial.
Discard unused portion.